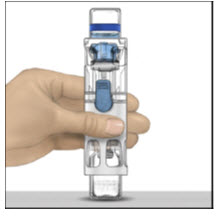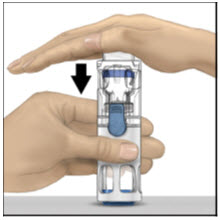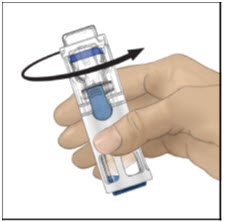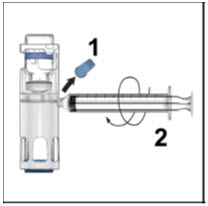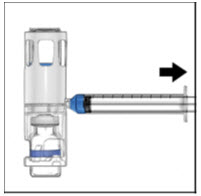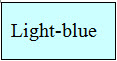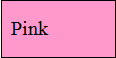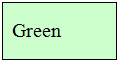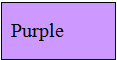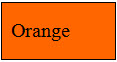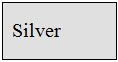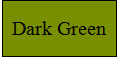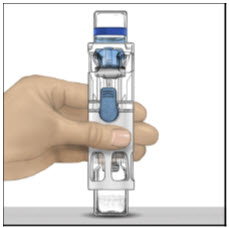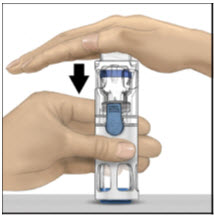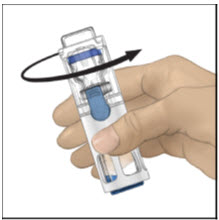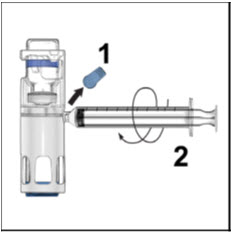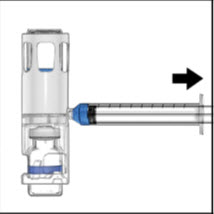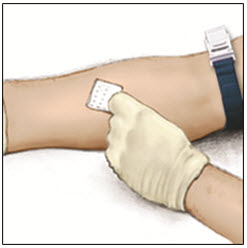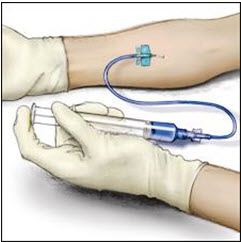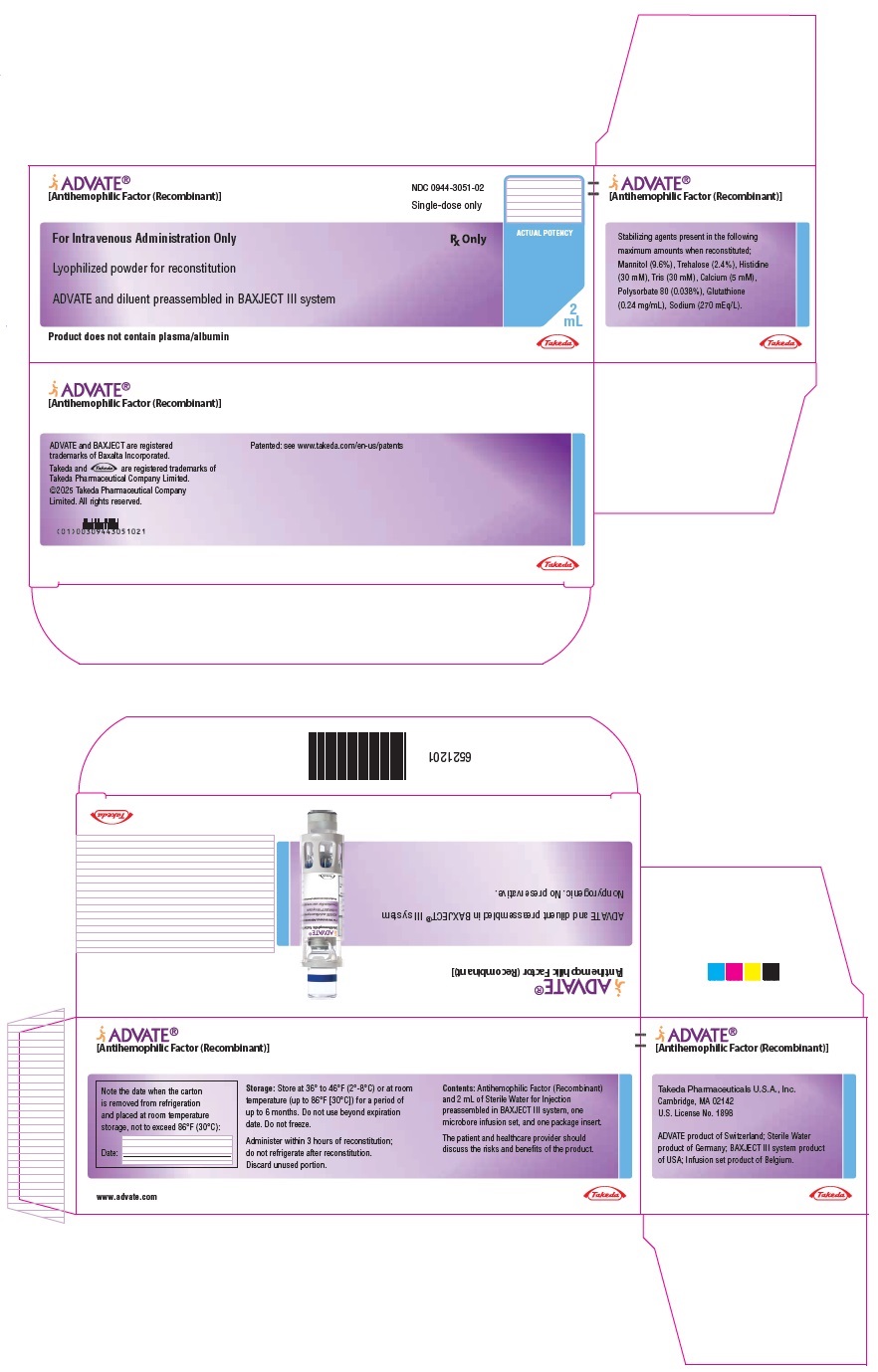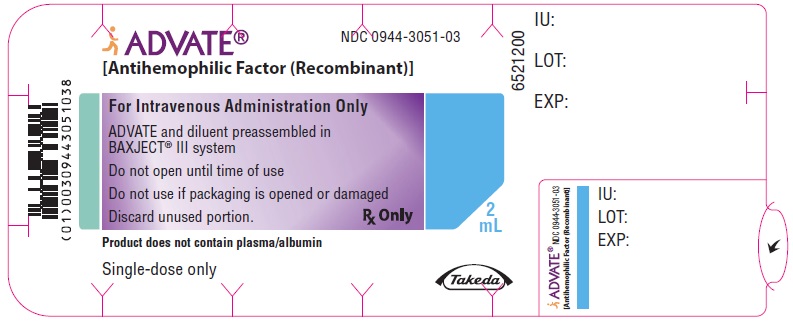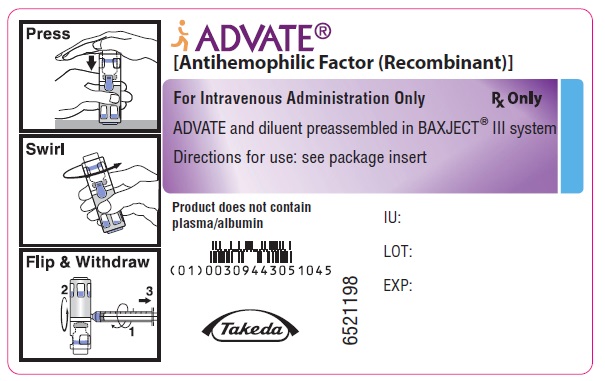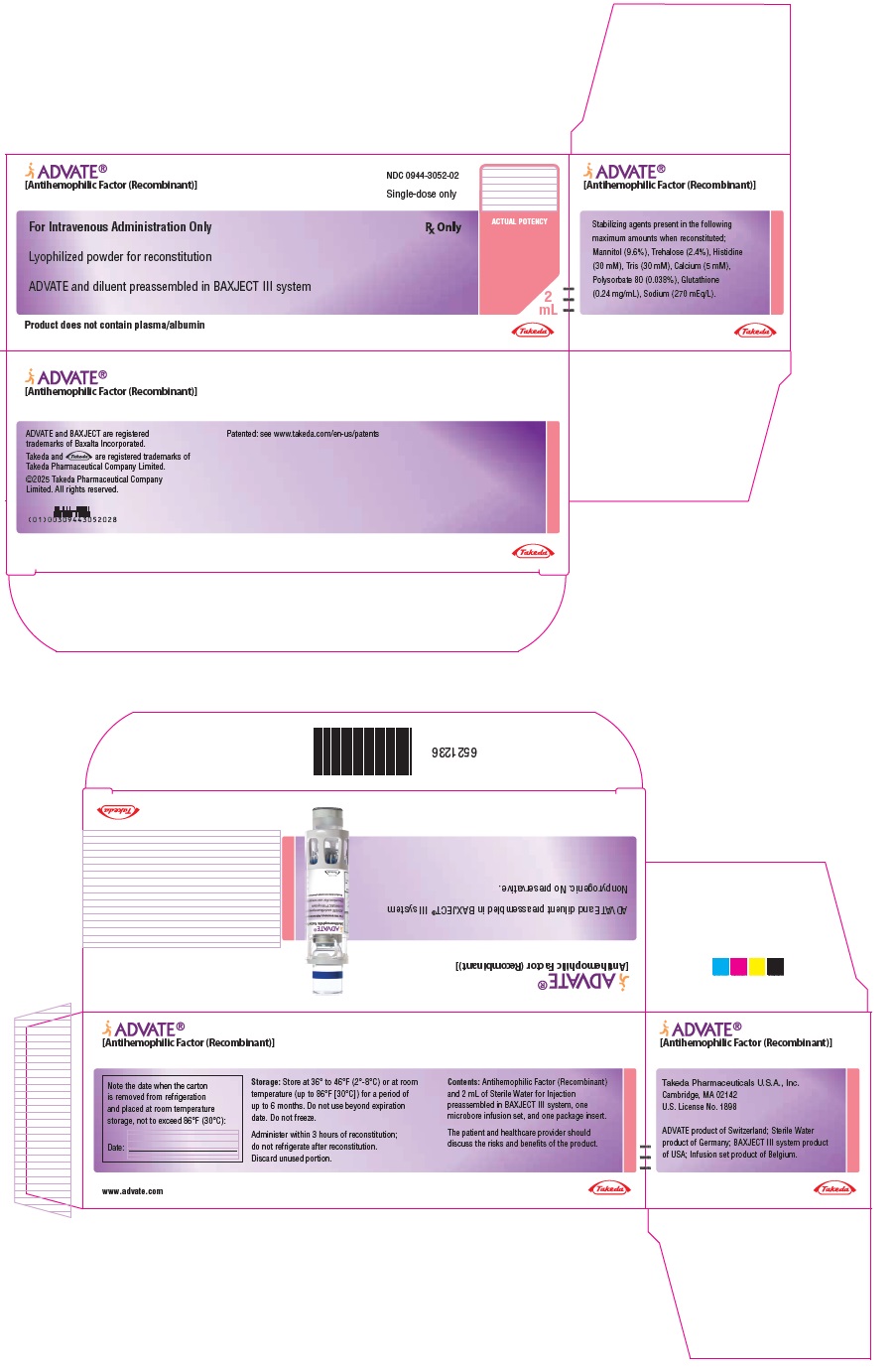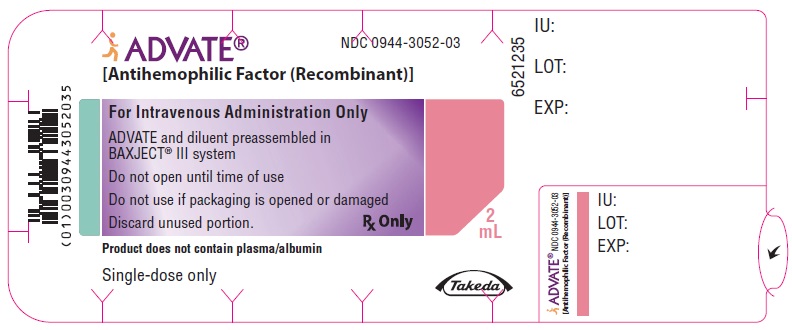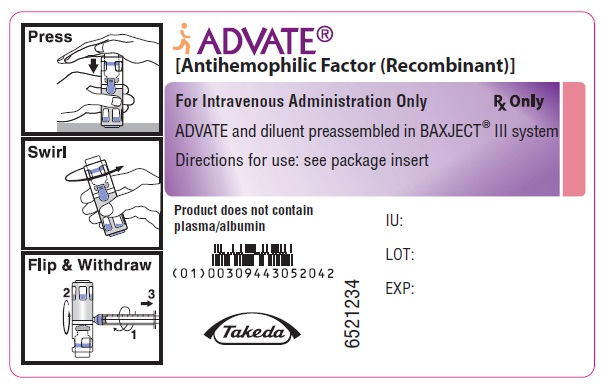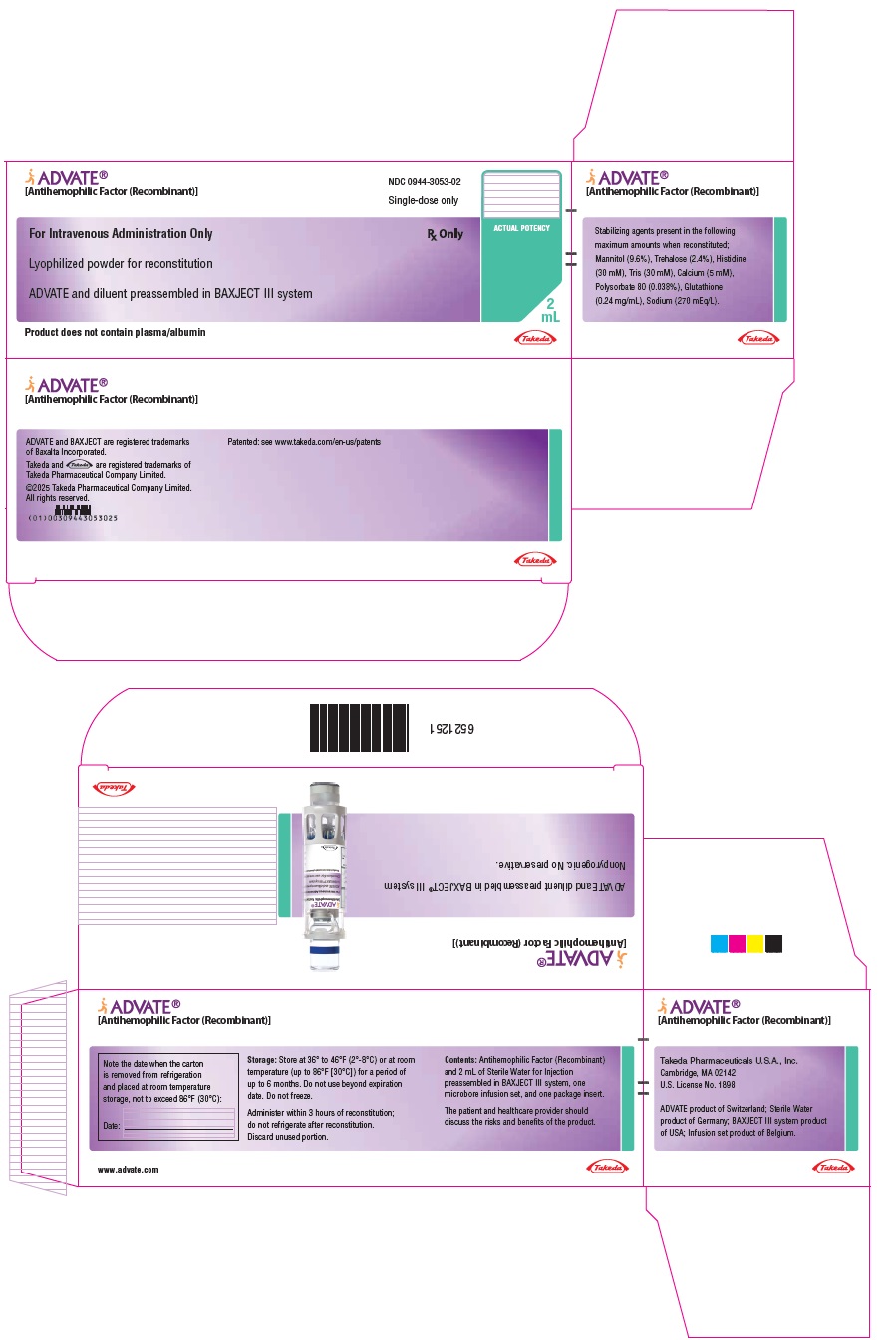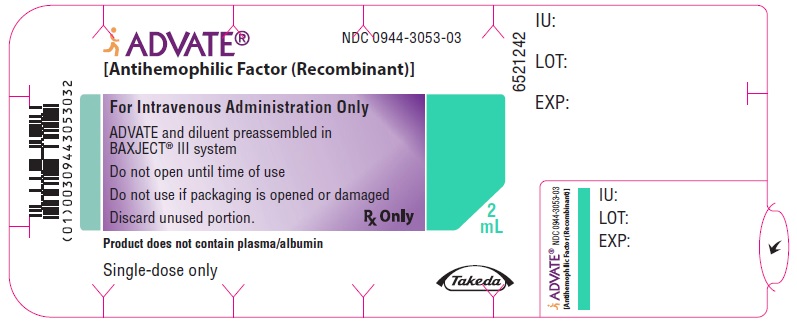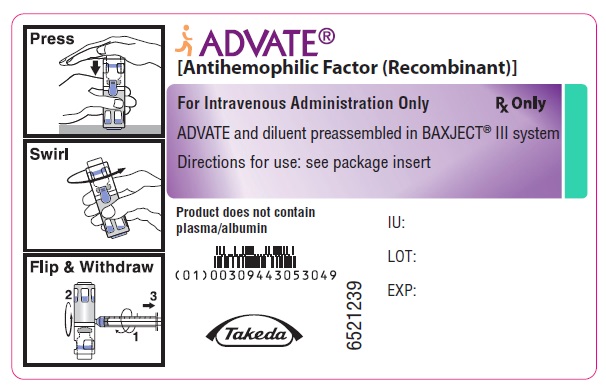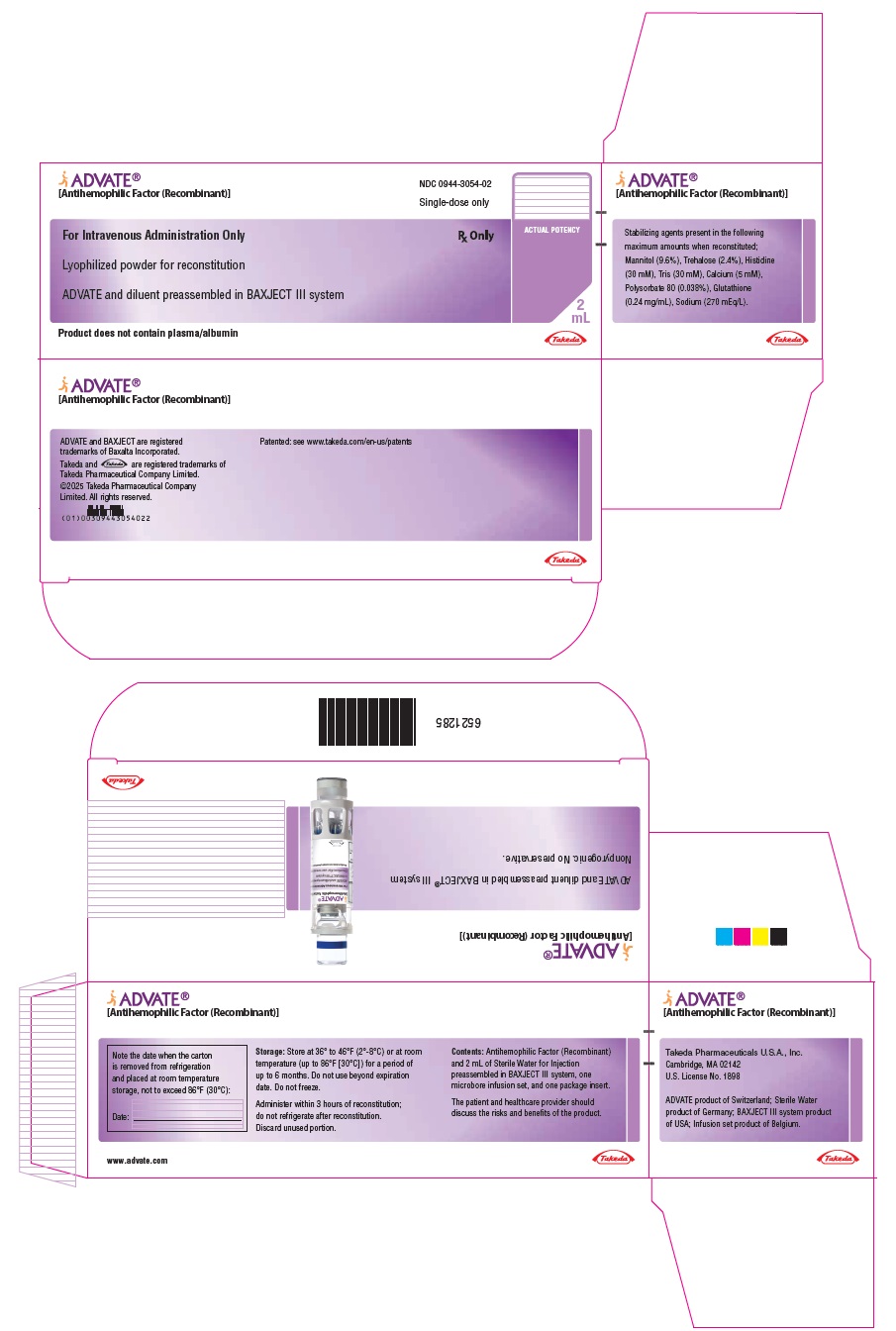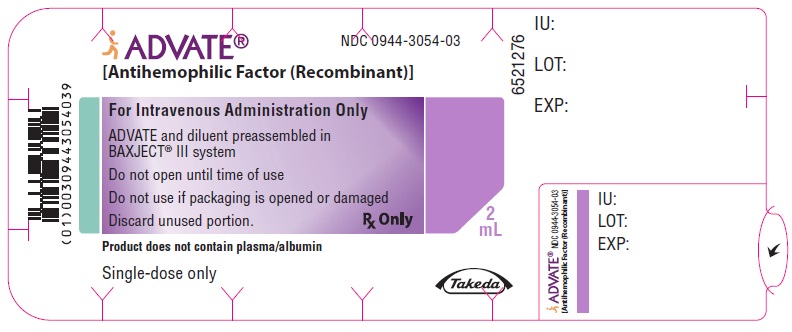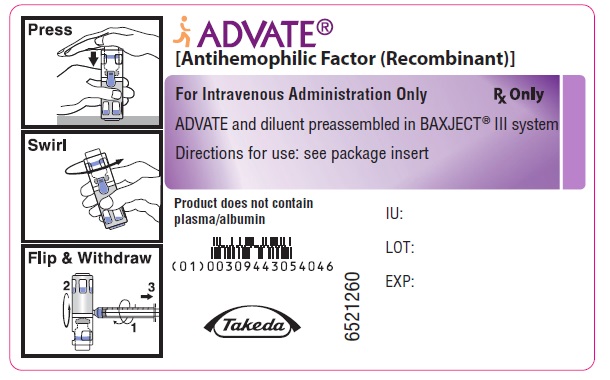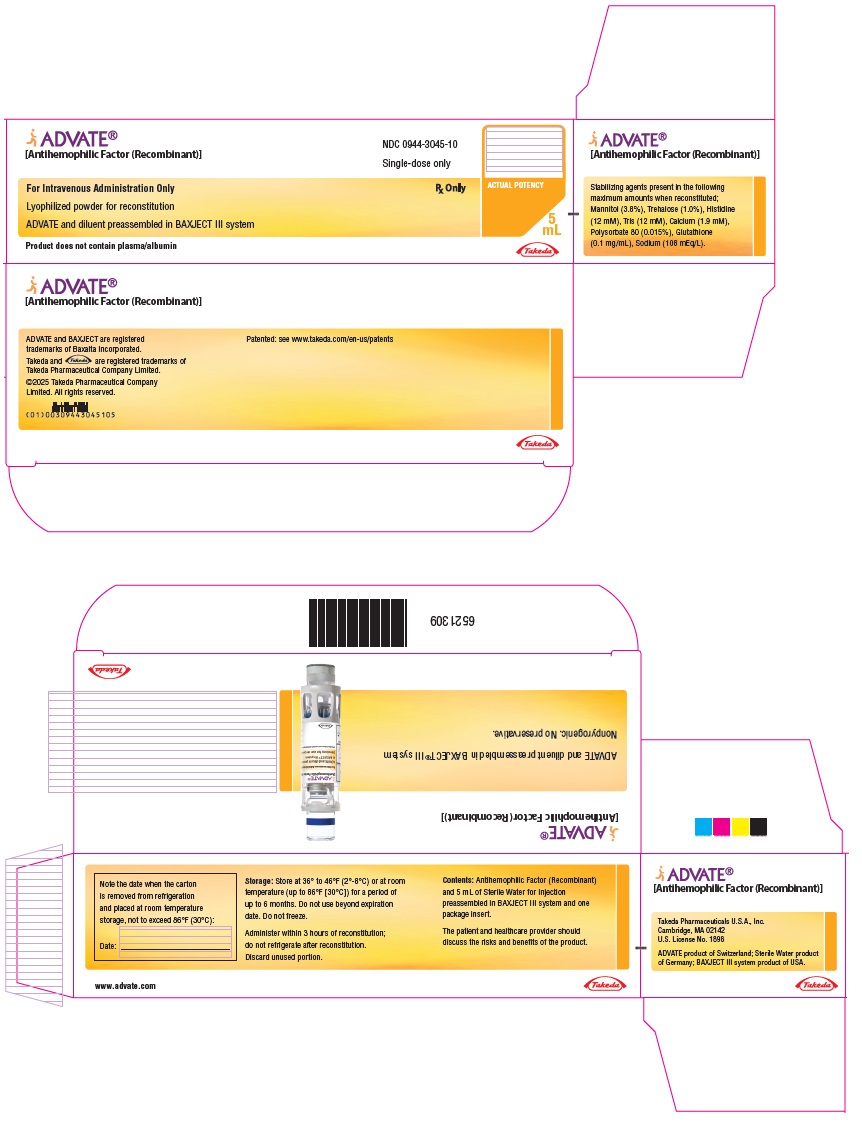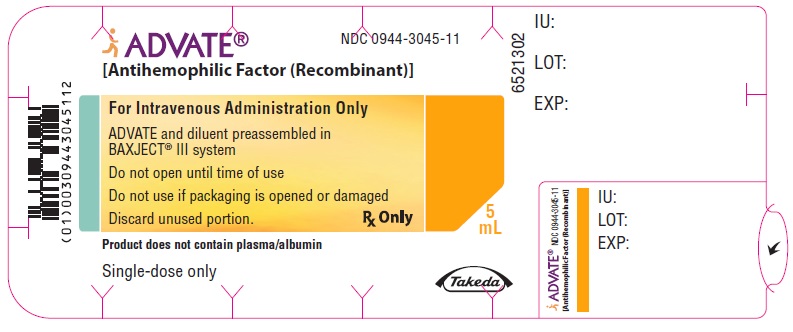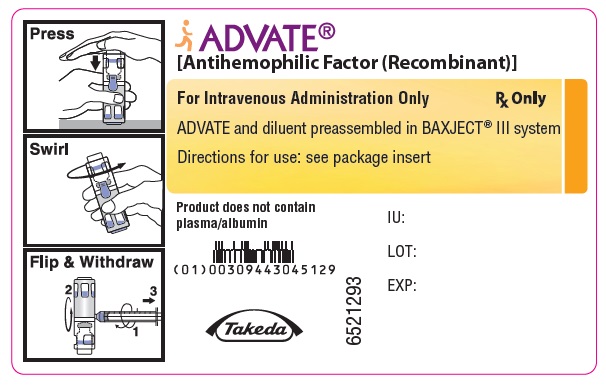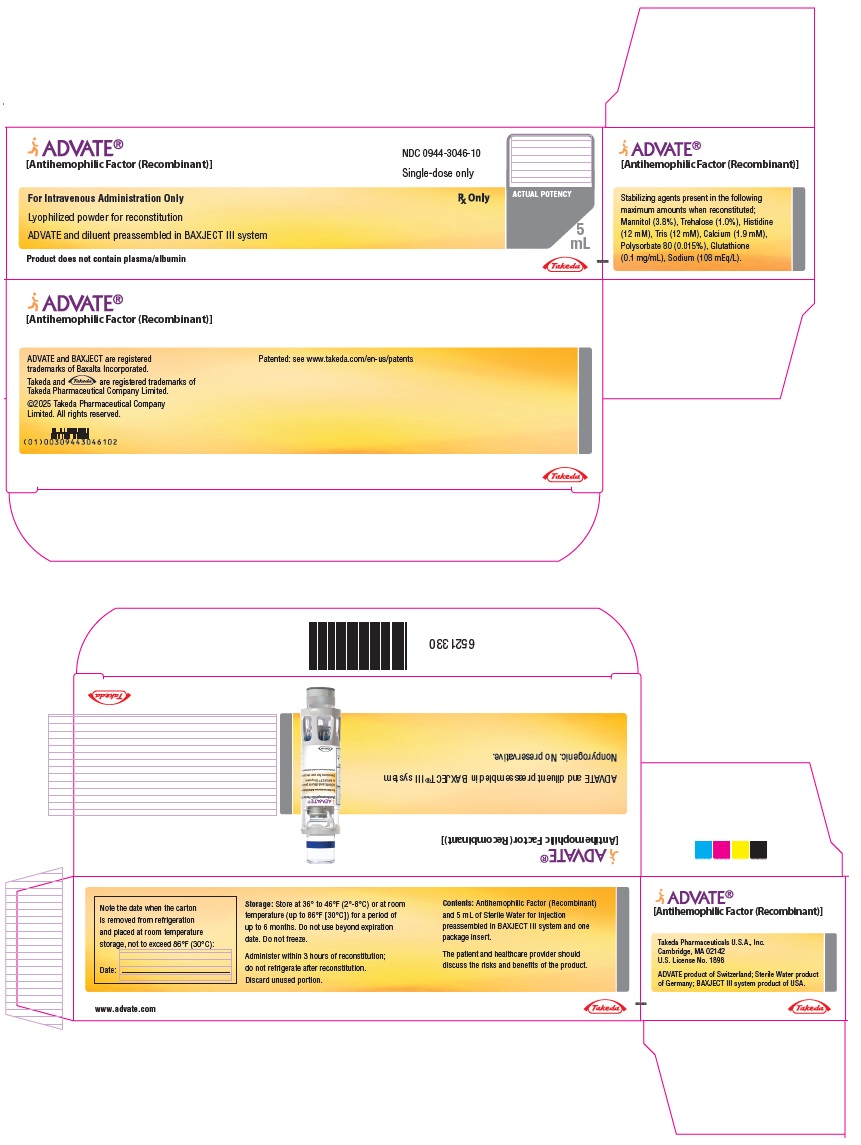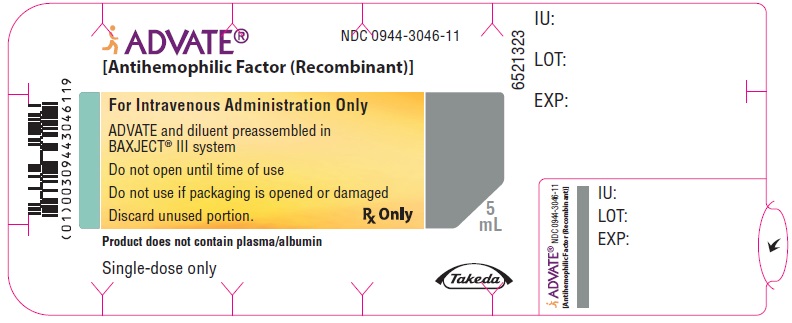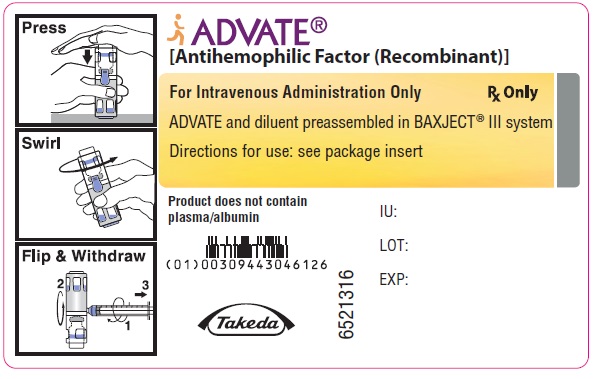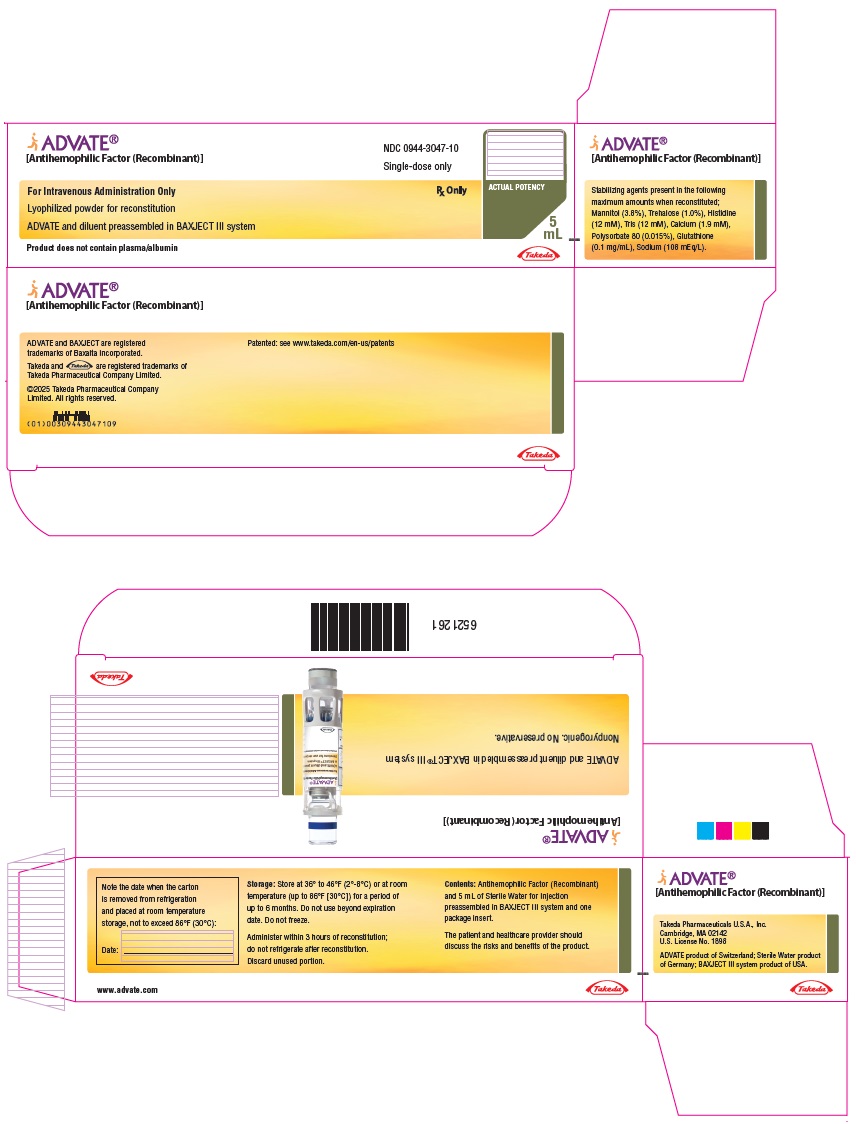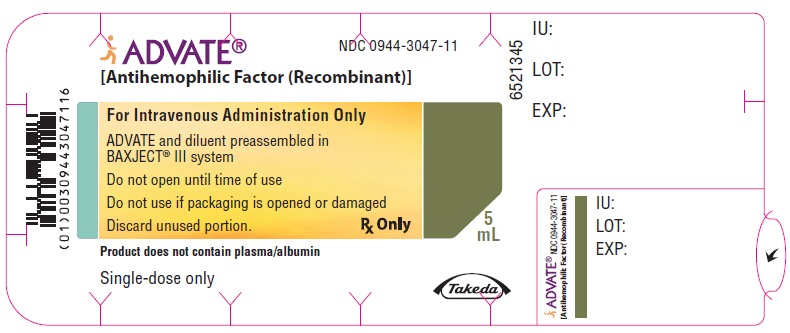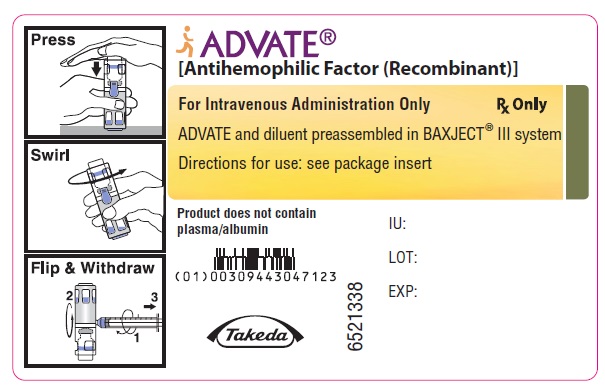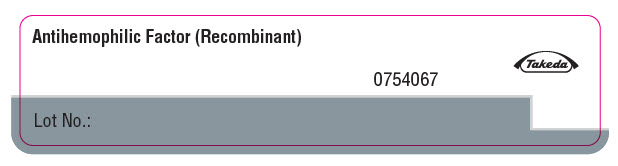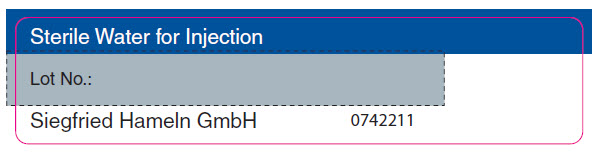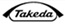 DRUG LABEL: ADVATE
NDC: 0944-3051 | Form: KIT | Route: INTRAVENOUS
Manufacturer: Takeda Pharmaceuticals America, Inc.
Category: other | Type: PLASMA DERIVATIVE
Date: 20250403

ACTIVE INGREDIENTS: ANTIHEMOPHILIC FACTOR, HUMAN RECOMBINANT 125 [iU]/1 mL
INACTIVE INGREDIENTS: MANNITOL; SODIUM CHLORIDE; HISTIDINE; CALCIUM CHLORIDE; POLYSORBATE 80; GLUTATHIONE; TREHALOSE; TROMETHAMINE; WATER 2 mL/2 mL

HIGHLIGHTS OF PRESCRIBING INFORMATION

These highlights do not include all the information needed to use ADVATE® safely and effectively. See full prescribing information for ADVATE.
ADVATE [antihemophilic factor (recombinant)] lyophilized powder for
reconstitution, for intravenous injection
Initial U.S. Approval: 2003

1 INDICATIONS AND USAGE

ADVATE is a recombinant antihemophilic factor indicated for use in children and adults with hemophilia A for:

- Control and prevention of bleeding episodes.
- Perioperative management.
- Routine prophylaxis to prevent or reduce the frequency of bleeding episodes.

ADVATE is not indicated for the treatment of von Willebrand disease. (1)

2 DOSAGE AND ADMINISTRATION

For intravenous injection after reconstitution only. (2)

Each vial of ADVATE contains the labeled amount of recombinant factor VIII in International Units (IU). (2.1)

Control and Prevention of Bleeding Episodes and Perioperative Management (2.1)

- Dose (IU) = body weight (kg) × desired factor VIII rise (IU/dL or % of normal) × 0.5 (IU/kg per IU/dL).
- Determine treatment frequency based on type of bleeding episode.

Routine Prophylaxis (2.1)

- 20 to 40 IU per kg every other day (3 to 4 times weekly).
- Alternatively, use every third day dosing regimen targeted to maintain FVIII trough levels ≥1%.

3 DOSAGE FORMS AND STRENGTHS

ADVATE is available as a lyophilized powder in single-dose vials containing nominally 250, 500, 1000, 1500, 2000, 3000, or 4000 IU. (3)

4 CONTRAINDICATIONS

Do not use in patients who have life-threatening hypersensitivity reactions, including anaphylaxis, to mouse or hamster protein or other constituents of the product (mannitol, trehalose, sodium chloride, histidine, Tris, calcium chloride, polysorbate 80, and/or glutathione). (4)

5 WARNINGS AND PRECAUTIONS

- Hypersensitivity reactions, including anaphylaxis, may occur. Patients may develop hypersensitivity to mouse or hamster protein, which is present in trace amounts in the product. Should symptoms occur, discontinue treatment with ADVATE and administer appropriate treatment. (5.1)
- Development of activity-neutralizing antibodies may occur. If expected plasma factor VIII activity levels are not attained, or if bleeding is not controlled with an appropriate dose, perform an assay that measures factor VIII inhibitor concentration. (5.2, 5.3)

6 ADVERSE REACTIONS

- Serious adverse drug reactions reported are hypersensitivity and factor VIII inhibitors. (6.1)
- The most common adverse drug reactions observed in greater than 5% of patients are pyrexia, headache, cough, nasopharyngitis, arthralgia, vomiting, upper respiratory tract infection, limb injury, nasal congestion, and diarrhea. (6.1)

To report SUSPECTED ADVERSE REACTIONS, contact Takeda Pharmaceuticals U.S.A., Inc. at 1-877-TAKEDA-7 (1-877-825-3327) or FDA at 1-800-FDA-1088 or www.fda.gov/medwatch.

8 USE IN SPECIFIC POPULATIONS

Pediatric Use: Clearance (based on per kg body weight) is higher in the pediatric population. Dose adjustment may be needed. (8.4)

FULL PRESCRIBING INFORMATION

1 INDICATIONS AND USAGE

ADVATE® [Antihemophilic Factor (Recombinant)] is a recombinant antihemophilic factor indicated for use in children and adults with hemophilia A (congenital factor VIII deficiency) for:

- Control and prevention of bleeding episodes.
- Perioperative management.
- Routine prophylaxis to prevent or reduce the frequency of bleeding episodes.

ADVATE is not indicated for the treatment of von Willebrand disease.

2 DOSAGE AND ADMINISTRATION

For intravenous injection after reconstitution only.

2.1 Dose

- Dosage and duration of treatment depend on the severity of factor VIII deficiency, the location and extent of the bleeding, and the patient's clinical condition. Careful control of replacement therapy is especially important in cases of major surgery or life-threatening bleeding episodes.
- Each vial of ADVATE has the recombinant factor VIII potency in International Units (IU) stated on the label. The expected in vivo peak increase in factor VIII level expressed as IU/dL of plasma or percent of normal can be estimated using the following formulas:
  IU/dL (or % of normal) = [total dose (IU)/body weight (kg)] × 2 [IU/dL]/[IU/kg]
  OR
  Required dose (International Units) = body weight (kg) × desired factor VIII rise (IU/dL or % of normal) × 0.5 (IU/kg per IU/dL)

Examples (assuming patient's baseline factor VIII level is <1% of normal):

1. A dose of 1750 IU ADVATE administered to a 70 kg patient should be expected to result in a peak postinfusion factor VIII increase of: 1750 IU × {[2 IU/dL]/[IU/kg]}/[70 kg] = 50 IU/dL (50% of normal).
2. A peak level of 70% is required in a 40 kg child. In this situation, the appropriate dose would be 40 kg × 70 IU/dL/{[2 IU/dL]/[IU/kg]} = 1400 IU.

- Base the dose and frequency on the individual clinical response. Patients may vary in their pharmacokinetic (e.g., half-life, in vivo recovery) and clinical responses to ADVATE. Although the dose can be estimated by the calculations above, whenever possible, perform appropriate laboratory tests including serial factor VIII activity assays [see Warnings and Precautions (5.3), Clinical Pharmacology (12.3)].

Control and Prevention of Bleeding Episodes

A guide for dosing ADVATE for the control and prevention of bleeding episodes is provided in Table 1. The goal of treatment is to maintain a plasma factor VIII activity level at or above the plasma levels (in % of normal or in IU/dL) outlined in Table 1.

Table 1: Dosing for Control and Prevention of Bleeding Episodes
Type of Bleeding Episodes | Factor VIII Level Required (% of normal or IU/dL) | Dose [Dose (IU/kg) = Desired factor VIII rise (IU/dL or % of normal) × 0.5 (IU/kg per IU/dL)] (IU/kg) | Frequency of Doses (hours) | Duration of Therapy (days)
Minor Early hemarthrosis, mild muscle bleeding, or mild oral bleeding episode. | 20 to 40 | 10 to 20 | 12 to 24 (Every 8 to 24 hours for patients under the age of 6) | Until the bleeding is resolved (approximately 1 to 3 days).
Moderate Muscle bleeding, bleeding into the oral cavity, definite hemarthroses, and known trauma. | 30 to 60 | 15 to 30 | 12 to 24 (Every 8 to 24 hours for patients under the age of 6) | Until the bleeding is resolved (approximately 3 days or more).
Major Significant gastrointestinal bleeding, intracranial, intra-abdominal or intrathoracic bleeding, central nervous system bleeding, bleeding in the retropharyngeal or retroperitoneal spaces or iliopsoas sheath, fractures, head trauma. | 60 to 100 | 30 to 50 | 8 to 24 (Every 6 to 12 hours for patients under the age of 6) | Until bleeding is resolved.

Perioperative Management

A guide for dosing ADVATE during surgery (perioperative management) is provided in Table 2. The goal of treatment is to maintain a plasma factor VIII activity level at or above the plasma level (in % of normal or in IU/dL) outlined in Table 2.

Table 2: Dosing for Perioperative Management
Type of Surgery | Factor VIII Level Required (% of normal or IU/dL) | Dose [Dose (IU/kg) = Desired factor VIII rise (IU/dL or % of normal) × 0.5 (IU/kg per IU/dL)] (IU/kg) | Frequency of Doses (hours) | Duration of Therapy (days)
Minor Including tooth extraction | 60 to 100 | 30 to 50 | Single dose within 1 hour of the operation. | Single dose or repeat until bleeding is resolved.
Minor Including tooth extraction |  |  | 12 to 24 (as needed to control bleeding) | For dental procedures, adjunctive therapy may be considered.
Major Intracranial, intra-abdominal, or intrathoracic surgery, joint replacement surgery | 80 to 120 (pre- and postoperative) | 40 to 60 | One dose preoperative to achieve 100% activity. Every 8 to 24 to keep factor VIII activity in desired range. (Every 6 to 24 hours for patients under the age of 6) | Until healing is complete.

Routine Prophylaxis

- Use dose of 20 to 40 International Units of factor VIII per kg body weight every other day (3 to 4 times weekly).
- Alternatively, use every third day dosing regimen targeted to maintain FVIII trough levels ≥1%.
- Adjust dose based on the patient's clinical response.^1,2

2.2 Preparation and Reconstitution

Preparation

- Do not remove ADVATE or diluent vials from the external housing.
- Always work on a clean surface and wash your hands before performing the procedures.
- Examine the packaging containing ADVATE to ensure no damage or peeling of the lid is evident. Do not use if the lid is not completely sealed on the blister. Do not remove ADVATE or diluent vials from the external housing.

Reconstitution

1. Allow the ADVATE package to reach room temperature.
2. Open the package by peeling away the lid. Remove ADVATE from the package and verify that the expiration date on the label has not passed and the potency unit number is same as expected. Inspect parenteral drug products for discoloration and particulate matter. The ADVATE powder should be white to off-white in color and the diluent free from foreign particles. Do not use if the criteria are not met.
3. Place the ADVATE on a flat surface with the diluent vial on top (Figure A). The diluent vial has a blue stripe. Do not remove the blue cap until instructed in a later step.
4. With one hand holding the ADVATE housing, press down firmly on the diluent vial with the other hand until the system is fully collapsed and the diluent flows down into the ADVATE vial (Figure B). Do not tilt the system until the transfer is complete.
5. Verify that diluent transfer is complete. Swirl gently until the powder is completely dissolved (Figure C). Do not shake. Do not refrigerate after reconstitution.

Figure A

Figure B

Figure C

2.3 Administration

For intravenous injection after reconstitution only.

- Inspect parenteral drug products for particulate matter and discoloration prior to administration. The solution should be clear and colorless in appearance. If not, do not use the solution and notify Takeda Pharmaceuticals U.S.A., Inc. immediately.
- Administer ADVATE at room temperature within 3 hours of reconstitution.
- Use plastic syringes with this product because proteins in the product tend to stick to the surface of glass syringes.

1. Use aseptic technique.
2. Remove the blue cap from the housing. Connect the syringe to the system (Figure D). Do not inject air into the ADVATE.
3. Turn the system upside down (factor concentrate vial now on top). Draw the factor concentrate into the syringe by pulling the plunger back slowly (Figure E).
4. Disconnect the syringe, attach a suitable needle, and inject intravenously as instructed. If a patient is to receive more than one ADVATE-BAXJECT® III system or a combination of an ADVATE-BAXJECT II and an ADVATE-BAXJECT III system, the contents may be drawn into the same syringe.
5. Administer ADVATE over a period of ≤5 minutes (maximum infusion rate 10 mL/min). Determine the pulse rate before and during administration of ADVATE. Should a significant increase in pulse rate occur, reducing the rate of administration or temporarily halting the injection usually allows the symptoms to disappear promptly.

Figure D

Figure E

3 DOSAGE FORMS AND STRENGTHS

ADVATE is available as a lyophilized white to off-white powder in single-dose vials containing nominally 250, 500, 1000, 1500, 2000, 3000, or 4000 International Units (IU, unit). The 250 to 1500 IU strengths come with 2 mL Sterile Water for Injection (sWFI); the 2000 to 4000 IU strengths come with 5 mL of sWFI.

Each ADVATE is labeled on the housing with the recombinant antihemophilic factor (rAHF) activity expressed in IU per system. This potency assignment employs a factor VIII concentrate standard that is referenced to a WHO (World Health Organization) international standard for factor VIII concentrates and is evaluated by appropriate methodology to ensure accuracy of the results.

4 CONTRAINDICATIONS

ADVATE is contraindicated in patients who have life-threatening hypersensitivity reactions, including anaphylaxis, to mouse or hamster protein or other constituents of the product (mannitol, trehalose, sodium chloride, histidine, Tris, calcium chloride, polysorbate 80, and/or glutathione).

5 WARNINGS AND PRECAUTIONS

5.1 Hypersensitivity Reactions

Allergic-type hypersensitivity reactions, including anaphylaxis, have been reported with ADVATE. Symptoms include dizziness, paresthesia, rash, flushing, facial swelling, urticaria, dyspnea, pruritus, and vomiting.

ADVATE contains trace amounts of mouse immunoglobulin G (MuIgG) ≤0.1 ng/IU ADVATE, and hamster proteins ≤1.5 ng/IU ADVATE. Patients treated with this product may develop hypersensitivity to these nonhuman mammalian proteins.

Discontinue ADVATE if hypersensitivity symptoms occur and administer appropriate emergency treatment.

5.2 Neutralizing Antibodies

Neutralizing antibodies (inhibitors) have been reported following administration of ADVATE predominantly in previously untreated patients (PUPs) and previously minimally treated patients (MTPs). Monitor all patients for the development of factor VIII inhibitors by appropriate clinical observation and laboratory testing. If expected plasma factor VIII activity levels are not attained, or if bleeding is not controlled with an expected dose, perform an assay that measures factor VIII inhibitor concentration [see Warnings and Precautions (5.3)].

5.3 Monitoring Laboratory Tests

- Monitor plasma factor VIII activity levels by the one-stage clotting assay to confirm the adequate factor VIII levels have been achieved and maintained when clinically indicated [see Dosage and Administration (2.1)].
- Monitor for development of factor VIII inhibitors. Perform the Bethesda assay to determine if factor VIII inhibitor is present. If expected factor VIII activity plasma levels are not attained, or if bleeding is not controlled with the expected dose of ADVATE, use Bethesda Units (BU) to titer inhibitors.
  - If the inhibitor titer is less than 10 BU per mL, the administration of additional antihemophilic factor concentrate may neutralize the inhibitor and may permit an appropriate hemostatic response.
  - If the inhibitor titer is above 10 BU per mL, adequate hemostasis may not be achieved. The inhibitor titer may rise following ADVATE infusion as a result of an anamnestic response to factor VIII. The treatment or prevention of bleeding in such patients requires the use of alternative therapeutic approaches and agents.

6 ADVERSE REACTIONS

Serious adverse reactions seen with ADVATE are hypersensitivity reactions, including anaphylaxis, and the development of high-titer inhibitors necessitating alternative treatments to factor VIII.

The most common adverse reactions observed in clinical trials (frequency greater than 5% of subjects) were pyrexia, headache, cough, nasopharyngitis, arthralgia, vomiting, upper respiratory tract infection, limb injury, nasal congestion, and diarrhea.

6.1 Clinical Trials Experience

Because clinical trials are conducted under widely varying conditions, adverse reaction rates observed in the clinical trials of a drug cannot be directly compared to rates in clinical trials of another drug and may not reflect the rates observed in clinical practice.

ADVATE has been evaluated in 11 clinical trials in previously treated patients (PTPs) and one trial in previously untreated patients (PUPs) with severe to moderately severe hemophilia A (factor VIII ≤2% of normal). A total of 418 subjects have been treated with ADVATE as of January 2012. Total exposure to ADVATE was 63,188 infusions. The median duration of participation per subject was 397 (min-max: 2−1620) days and the median number of exposure days to ADVATE per subject was 97 (min-max: 1−709).

The summary of adverse reactions with a frequency >5% are shown in Table 3 below.

No subject was withdrawn from a clinical trial due to an adverse reaction.

Table 3: Summary of Adverse Reactions (ARs) [Adverse reactions are defined as all adverse events that occurred (a) within 24 hours after being infused with investigational product, or (b) all adverse events assessed related or possibly related to investigational product, or (c) adverse events for which the investigator's or sponsor's opinion of causality was missing or indeterminate.] with a Frequency Greater than 5% in 418 [The ADVATE clinical program included 418 treated subjects from 11 completed studies in PTPs and 1 completed trial in PUPs.] Subjects
MedDRA [MedDRA version 8.1 was used.] System Organ Class | MedDRA Preferred Term | Number of Adverse Reactions | Number of Subjects | Percent of Subjects
General Disorders and Administration Site Conditions | Pyrexia | 110 | 66 | 16
Nervous System Disorders | Headache | 114 | 56 | 13
Respiratory, Thoracic and Mediastinal Disorders | Cough | 86 | 54 | 13
Infections and Infestations | Nasopharyngitis | 72 | 49 | 12
Musculoskeletal and Connective Tissue Disorders | Arthralgia | 49 | 32 | 8
Gastrointestinal Disorders | Vomiting | 41 | 31 | 7
Infections and Infestations | Upper Respiratory Tract Infection | 35 | 29 | 7
Injury, Poisoning and Procedural Complications | Limb Injury | 56 | 25 | 6
Respiratory, Thoracic and Mediastinal Disorders | Nasal Congestion | 32 | 25 | 6
Gastrointestinal Disorders | Diarrhea | 29 | 24 | 6
Injury, Poisoning and Procedural Complications | Procedural Pain | 26 | 22 | 5
Respiratory, Thoracic and Mediastinal Disorders | Oropharyngeal Pain | 25 | 22 | 5
Infections and Infestations | Ear Infection | 30 | 21 | 5

Immunogenicity

The development of factor VIII inhibitors with the use of ADVATE was evaluated in clinical trials with pediatric PTPs (<6 years of age with ≥50 factor VIII exposures) and PTPs (≥10 years of age with ≥150 factor VIII exposures). Of 276 subjects who were treated with ADVATE for at least 10 exposure days or on study for a minimum of 120 days, 1 adult developed a low-titer inhibitor (2 BU in the Bethesda assay) after 26 exposure days. Eight weeks later, the inhibitor was no longer detectable, and in vivo recovery was normal at 1 and 3 hours after infusion of another marketed recombinant factor VIII concentrate. This event results in a factor VIII inhibitor frequency in PTPs of 0.4% (95% CI of 0.01 and 2% for the risk of any factor VIII inhibitor development).^3 No factor VIII inhibitors were detected in the 53 treated pediatric PTPs.

In clinical trials that enrolled previously untreated subjects (defined as having had up to 3 exposures to a factor VIII product at the time of enrollment), 16 (29.1%) of 55 subjects who received ADVATE developed inhibitors to factor VIII. Seven subjects developed high-titer (>5 BU) and nine subjects developed low-titer inhibitors. Inhibitors were detected at a median of 13 exposure days (min-max: 6 to 26 exposure days) to the product.

Immunogenicity also was evaluated by measuring the development of antibodies to heterologous proteins. When assessed for anti-Chinese hamster ovary (CHO) cell protein antibodies, of 229 treated subjects, 3 showed an upward trend in antibody titer over time and 10 showed repeated but transient elevations of antibodies. When assessed for muIgG protein antibodies, of the 229 treated subjects, 10 showed an upward trend in anti-muIgG antibody titer over time and 2 showed repeated but transient elevations of antibodies. Four subjects who demonstrated antibody elevations to CHO cell or muIgG proteins, reported isolated events of urticaria, pruritus, rash, and slightly elevated eosinophil counts. All of these subjects had numerous repeat exposures to the product without recurrence of the events and a causal relationship between the antibody findings and these clinical events has not been established.

When assessed for the presence of anti-human von Willebrand Factor (VWF) antibodies, of the 228 treated subjects, none displayed laboratory evidence indicative of a positive serologic response.

The detection of antibody formation is highly dependent on the sensitivity and specificity of the assay. Additionally, the observed incidence of antibody (including neutralizing antibody) positivity in an assay may be influenced by several factors including assay methodology, sample handling, timing of sample collection, concomitant medications, and underlying disease. For these reasons, comparison of the incidence of antibodies to ADVATE with the incidence of antibodies to other products may be misleading.

6.2 Postmarketing Experience

The following adverse reactions have been identified during postapproval use of ADVATE. Because these reactions are reported voluntarily from a population of uncertain size, it is not always possible to reliably estimate their frequency or establish a causal relationship to drug exposure.

Table 4 represents the most frequently reported postmarketing adverse reactions as MedDRA Preferred Terms.

Table 4: Postmarketing Experience
Organ System [MedDRA Primary SOC] | Preferred Term
Immune System Disorders | Anaphylactic reaction Hypersensitivity
General Disorders and Administration Site Conditions | Injection site reaction Chills Fatigue/Malaise Chest discomfort/pain Decreased therapeutic effect

8 USE IN SPECIFIC POPULATIONS

8.1 Pregnancy

Risk Summary

There are no data with ADVATE use in pregnant women to inform a drug-associated risk. Animal reproduction studies have not been conducted with ADVATE. It is not known whether ADVATE can cause fetal harm when administered to a pregnant woman or whether it can affect reproductive capacity.

In the U.S. general population, the estimated background risk of major birth defect and miscarriage in clinically recognized pregnancies is 2 to 4% and 15 to 20%, respectively.

8.2 Lactation

Risk Summary

There is no information regarding the presence of ADVATE in human milk, the effect on the breastfed infant, or the effects on milk production.

The developmental and health benefits of breastfeeding should be considered along with the mother's clinical need for ADVATE and any potential adverse effects on the breastfed child from ADVATE or from the underlying maternal condition.

8.4 Pediatric Use

Pharmacokinetic studies in children have demonstrated higher clearance, a shorter half-life and lower recovery of factor VIII compared to adults [see Clinical Pharmacology (12.3)]. This may be explained by differences in body composition and should be taken into account when dosing or following factor VIII levels in the pediatric population.^4 Because clearance (based on per kg body weight) has been demonstrated to be higher in the pediatric population, dose adjustment or more frequent dosing based on per kg body weight may be needed in this population [see Clinical Pharmacology (12.3)]. In the ADVATE routine prophylaxis clinical trial, 3 children aged 7 to <12 and 4 adolescents aged 12 to <16 were included in the per-protocol analysis. The reductions in annualized bleeding rate per subject per year during any prophylaxis regimen as compared to during on-demand therapy were similar among children, adolescents, and adults [see Clinical Studies (14)].

8.5 Geriatric Use

Clinical trials of ADVATE did not include sufficient numbers of subjects aged 65 and over to determine whether they respond differently from younger subjects. Other reported clinical experience has not identified differences in responses between the elderly and younger patients. In general, dose selection for an elderly patient should be cautious, usually starting at the low end of the dosing range, reflecting the greater frequency of decreased hepatic, renal, or cardiac function, and of concomitant disease and other drug therapy.

11 DESCRIPTION

ADVATE [Antihemophilic Factor (Recombinant)] is a purified glycoprotein consisting of 2,332 amino acids that is synthesized by a genetically engineered Chinese hamster ovary (CHO) cell line but does not contain plasma or albumin. The CHO cell line employed in the production of ADVATE is derived from that used in the biosynthesis of RECOMBINATE® [Antihemophilic Factor (Recombinant)]. ADVATE has been shown to be comparable to RECOMBINATE with respect to its biochemical and physicochemical properties, as well as its nonclinical in vivo pharmacology.

In culture, the CHO cell line expresses the recombinant antihemophilic factor (rAHF) into the cell culture medium. The rAHF is purified from the culture medium using a series of chromatography columns. The purification process includes an immunoaffinity chromatography step in which a monoclonal antibody directed against factor VIII is employed to selectively isolate the rAHF from the medium. The cell culture and purification processes used in the manufacture of ADVATE employ no additives of human or animal origin. The production process includes a dedicated, viral inactivation solvent-detergent treatment step. The rAHF synthesized by the CHO cells has the same biological effects on clotting as human antihemophilic factor (hAHF). Structurally, the recombinant protein has a similar combination of heterogeneous heavy and light chains as found in AHF (Human).

ADVATE is formulated as a sterile, nonpyrogenic, white to off-white powder for intravenous injection. ADVATE in a single-dose vial contains nominally 250, 500, 1000, 1500, 2000, 3000, or 4000 International Units (IU). The product contains the following stabilizers and excipients: mannitol, trehalose, sodium chloride, histidine, Tris, calcium chloride, polysorbate 80, and glutathione. Von Willebrand factor (VWF) is co-expressed with factor VIII and helps to stabilize it in culture. The final product contains no more than 2 ng VWF/IU rAHF, which will not have any clinically relevant effect in patients with von Willebrand disease.

The product contains no preservative. When reconstituted with the provided Sterile Water for Injection, USP, the final solution contains the following stabilizers and excipients in targeted amounts:

Table 5: Approximate Concentration of Stabilizer and Excipient after Reconstitution
Stabilizer and Excipient | 2 mL Reconstitution (for 250, 500, 1000, 1500 IU) Target | 5 mL Reconstitution (for 2000, 3000, 4000 IU) Target
Tris (hydroxymethyl) aminomethane | 25 mM | 10 mM
Calcium Chloride | 4.2 mM | 1.7 mM
Mannitol | 8% (w/v) | 3.2% (w/v)
Sodium Chloride | 225 mM | 90 mM
α, α-Trehalose | 2% (w/v) | 0.8% (w/v)
Histidine | 25 mM | 10 mM
Glutathione (Reduced) | 0.2 mg/mL | 0.08 mg/mL
Polysorbate 80 | 0.025% (w/v) | 0.01% (w/v)

Each ADVATE housing is labeled with the rAHF activity expressed in international units. Biological potency is determined by an in vitro assay, which employs a factor VIII concentrate standard that is referenced to a WHO international standard for factor VIII concentrates. One international unit, as defined by the WHO standard for blood coagulation factor VIII, human, is approximately equal to the level of factor VIII activity found in 1 mL of fresh pooled human plasma. The specific activity of ADVATE is 4000 to 10000 International Units per milligram of protein.

12 CLINICAL PHARMACOLOGY

12.1 Mechanism of Action

ADVATE temporarily replaces the missing coagulation factor VIII that is needed for effective hemostasis.

12.2 Pharmacodynamics

The activated partial thromboplastin time (aPTT) is prolonged in patients with hemophilia. Determination of aPTT is a conventional in vitro assay for biological activity of factor VIII. Treatment with ADVATE normalizes the aPTT over the effective dosing period.

12.3 Pharmacokinetics

A randomized, crossover pharmacokinetic trial of ADVATE (test) and RECOMBINATE [Antihemophilic Factor (Recombinant)] (reference) was conducted in 56 nonbleeding subjects. The subjects received either of the products as an IV infusion (50 ± 5 IU/kg body weight) and there was a washout period of 72 hours to 4 weeks between the two infusions. The pharmacokinetic parameters were calculated from factor VIII activity measurements in blood samples obtained up to 48 hours following each infusion.^3 The per-protocol analysis included 30 patients (20 adults and 10 children). Pharmacokinetic parameters for the 20 adults for each trial are presented in Table 6.

Table 6: Pharmacokinetic Parameters (Mean ± SD) for ADVATE and RECOMBINATE (N=20 Adult Subjects Age >16 years)
Parameter | RECOMBINATE (N=20) | ADVATE (N=20)
AUC0-48h (IU∙hrs/dL) [Area under the plasma factor VIII concentration × time curve from 0 to 48 hours postinfusion.] | 1638 ± 357 | 1644 ± 338
In vivo recovery (IU/dL/IU/kg) [Calculated as (Cmax – baseline factor VIII) divided by the dose in IU/kg, where Cmax is the maximal postinfusion factor VIII measurement.] | 2.7 ± 0.6 | 2.6 ± 0.5
Half-life (hrs) | 11.2 ± 2.5 | 12.0 ± 4.2
Cmax (IU/dL) | 136 ± 29 | 128 ± 28
MRT (hrs) | 14.7 ± 3.8 | 15.8 ± 5.9
Vss (dL/kg) | 0.4 ± 0.1 | 0.4 ± 0.1
CL (mL/kg*hr) | 3 ± 1 | 3 ± 1

The 90% confidence intervals for the ratios of the mean AUC(0-48h) and in vivo recovery values for the test and control products were within the pre-established limits of 0.80 and 1.25. In addition, in vivo recoveries at the onset of treatment and after 75 exposure days were compared for 62 subjects. Results of this analysis indicated no significant change in the in vivo recovery at the onset of treatment and after ≥75 exposure days.

In an analysis of data from 58 subjects with 65 surgical procedures in the perioperative management trial, the target factor VIII level was met or exceeded in all cases following a single loading dose ranging from 29 to 104 IU/kg.

Pharmacokinetic parameters calculated from 98 subjects less than 16 years of age (intent-to-treat analysis) are available for 7 infants (1 month to less than 2 years), 32 children (2 to less than 5 years), 24 older children (5 to less than 12 years), and 35 adolescents (12 to less than 16 years), as shown in Table 7. The mean clearance (based on body weight) of ADVATE in infants, children, older children, and adolescents was higher than adults (3.6 mL/kg*hr). The mean half-life of ADVATE in infants, children, older children, and adolescents was lower than adults (12 hours). The extent to which these differences may be clinically significant is not known.

Table 7: Pharmacokinetic Parameters (Mean ± SD) of ADVATE by Age Group < 16 Years (N=98; Intent-to-Treat PK Analysis Set)
PK Parameter | Infants (N=7) (1 month to <2 yrs) | Children (N=32) (2 to <5 yrs) | Older Children (N=24) (5 to <12 yrs) | Adolescents (N=35) (12 to <16 yrs)
AUC0-inf (IU*hr/dL) | 1240 ± 330 | 1164 ± 424 | 1396 ± 506 | 1300 ± 469
Incremental Recovery at Cmax [Incremental recovery at Cmax calculated as (Cmax – baseline factor VIII) divided by the dose in IU/kg, where Cmax is the maximal postinfusion factor VIII measurement.] (IU/dL per IU/kg) | 2.1 ± 0.5 | 1.8 ± 0.4 | 2.1 ± 0.6 | 2.1 ± 0.5
Half-Life (hr) | 8.7 ± 1.4 | 9.5 ± 1.8 | 11.2 ± 3.5 | 12.0 ± 2.9
Maximum Plasma Concentration Postinfusion (IU/dL) | 104 ± 27 | 91 ± 19 | 105 ± 34 | 103 ± 25
Mean Residence Time (hr) | 10.4 ± 2.5 | 11.8 ± 2.8 | 14.3 ± 4.3 | 14.9 ± 4.6
Volume of Distribution at Steady State (dL/kg) | 0.4 ± 0.1 | 0.5 ± 0.1 | 0.6 ± 0.2 | 0.6 ± 0.1
Clearance (mL/kg*hr) | 4.3 ± 1.0 | 4.8 ± 1.5 | 4.1 ± 1.5 | 4.2 ± 1.2

In a crossover pharmacokinetic trial of recombinant antihemophilic factor, plasma/albumin free method (rAHF-PFM) reconstituted in 2 mL vs 5 mL Sterile Water for Injection, USP (sWFI) in previously treated severe hemophilia A adult and adolescent patients, the AUCs of the two formulations were comparable and the 90% confidence interval ranged from 90.4 to 102.6, indicating that the two formulations are pharmacokinetically equivalent.

13 NONCLINICAL TOXICOLOGY

13.1 Carcinogenesis, Mutagenesis, Impairment of Fertility

No studies have been conducted with the active ingredient in ADVATE to assess its mutagenic or carcinogenic potential.

RECOMBINATE was tested for mutagenicity at doses considerably exceeding plasma concentrations in vitro, and at doses up to ten times the expected maximal clinical dose in vivo. At that concentration, it did not cause reverse mutations, chromosomal aberrations, or an increase in micronuclei formation in bone marrow polychromatic erythrocytes. Studies in animals have not been performed to evaluate carcinogenic potential.

13.2 Animal Toxicology and/or Pharmacology

Single doses up to 4,750 IU/kg did not demonstrate any acute or toxic effect for ADVATE in laboratory animals (rat and rabbit).

14 CLINICAL STUDIES

Original Safety and Efficacy Study

A safety and efficacy trial evaluated the pharmacokinetics (double-blinded, randomized, crossover), safety, immunogenicity, and hemostatic efficacy (open-label) of ADVATE in 111 subjects. The trial was conducted in the US and Europe with 103 Caucasian, 7 Black, and 1 Asian previously treated subjects (PTPs with ≥150 exposure days) diagnosed with moderate to severe hemophilia A (FVIII level ≤2% of normal) who were ≥10 years of age (20 were 10 to <13, 22 were 13 to <16, and 69 were 16 years and older). Subjects with a history of, or a detectable FVIII inhibitor were excluded.

Subjects self-administered ADVATE for routine prophylaxis (≥25 IU/kg body weight 3 to 4 times per week) and for the on-demand treatment of bleeding episodes. A global assessment of efficacy was rendered by the subject (for home treatment) or study site investigator (for treatment under medical supervision) using a scale of excellent, good, fair, or none, based on the quality of hemostasis achieved with ADVATE for the treatment of each new bleeding episode.

A total of 510 bleeding episodes were reported, with a mean (± SD) of 6.1 ± 8.2 bleeding episodes per subject. Of these 510 episodes, 439 (86%) were rated excellent or good in their response to treatment with ADVATE, 61 (12%) were rated fair, 1 (0.2%) was rated as having no response, and for 9 (2%), the response to treatment was unknown. A total of 411 (81%) bleeding episodes were managed with a single infusion, 62 (12%) required 2 infusions, 15 (3%) required 3 infusions, and 22 (4%) required 4 or more infusions of ADVATE for satisfactory resolution. A total of 162 (32%) bleeding episodes occurred spontaneously, 228 (45%) were the result of antecedent trauma, and for 120 (24%) bleeding episodes, the etiology was unknown.^3

The rate of new bleeding episodes during the 75-exposure-day prophylactic regimen was calculated as a function of the etiology of bleeding episodes for 107 evaluable subjects (n = 274 bleeding episodes).^3 These rates are presented in Table 8. The overall rate of new bleeding episodes in the prophylaxis study was 0.52 ± 0.71.

Table 8: Rate of New Bleeding Episodes During Prophylaxis
Types of Bleeding Episode | Mean (± SD) New Bleeding Episodes/Subject/Month
Spontaneous | 0.34 ± 0.49
Post-traumatic | 0.39 ± 0.46
Unknown/Indeterminate | 0.33 ± 0.34

The pharmacokinetic properties of ADVATE were investigated at the beginning of treatment in a multicenter trial of previously treated subjects and at the end of treatment in a subset of subjects (N=34) who had completed at least 75 exposure days of treatment with ADVATE [see Clinical Pharmacology (12.3)].

Continuation Study

Additional (open-label) safety and efficacy data were collected on 82 subjects who continued with treatment following participation in the original safety and efficacy study. Bleeding episodes were treated with ADVATE and the outcome of treatment was rated as excellent, good, fair, or none, based on the quality of hemostasis achieved. Final analysis of efficacy was conducted for 81 subjects who self-administered ADVATE on a routine prophylactic regimen for a minimum period of 75 exposure days.

A total of 837 bleeding episodes occurred in 70 of the 81 subjects. The other 11 subjects experienced no bleeding episodes. The response to treatment with ADVATE was rated as excellent or good for 80.4% of all bleeding episodes. Most (88%) bleeding episodes required only 1 or 2 infusions to obtain hemostasis. Among the 837 bleeding episodes, 2 (0.3%) did not require treatment (0 infusions), 521 (62.2%) required 1 infusion, 216 (25.8%) required 2 infusions, 23 (2.7%) required 3 infusions, and 75 (9.0%) required 4 or more infusions. By etiology, 45.3% of these bleeding events were secondary to trauma and 27.7% occurred spontaneously; the other 27% had an undetermined etiology.

In vivo recoveries at the onset of treatment and after 75 exposure days were compared for 62 subjects and there were no significant differences.

Perioperative Management Study

The safety and efficacy of ADVATE for perioperative management was investigated in 59 subjects with severe or moderately severe hemophilia A (factor VIII ≤2%). They were between the ages of 7 to 65 years of age (3 were 7 to <13, 6 were 13 to <16, and 50 were ≥16). Fifty-five were Caucasian, 3 were Black, and 1 was Asian. One subject elected not to undergo the planned surgery. Thus, 58 subjects underwent 65 surgical procedures, among which, 6 subjects underwent more than 1 procedure each. One subject withdrew during the postoperative period; thus, 57 subjects completed the study. Of the 65 procedures, 22 in 22 subjects were classified as major, 35 in 28 subjects were classified as minor, and 8 in 8 subjects were dental. (See Table 2 for definitions of major and minor).

Prior to surgery, subjects received a pre-operative loading dose aimed at increasing the plasma factor VIII level to 60 to 100% of normal for dental procedures or 80 to 120% of normal for all other surgical procedures. During the surgery, subjects received replacement therapy by either bolus (47 procedures) or continuous infusion (18 procedures). For continuous infusion, the initial rate was 4 IU/kg/hr for subjects >12 years of age and 5 IU/kg/hr for subjects 5 to 12 years of age. After discharge, subjects continued to receive ADVATE for control of hemostasis as prescribed by the investigator for up to 6 weeks for major orthopedic procedures and up to 2 weeks for all other procedures.

Intraoperative efficacy was rated as excellent or good (Excellent intraoperative blood loss was less than expected for the type of procedure performed; Good intraoperative blood loss was as expected for the type of procedure performed) for 61 (93.9%) of the 65 procedures; the rating was not done for 3 procedures and unknown for 1 procedure. Postoperative efficacy was rated as excellent or good for 62 (95.4%) of the 65 procedures; the rating was unknown for 2 procedures and not done for 1 procedure. Of the 24 procedures requiring surgical drains, efficacy assessments at the time of drain removal were rated as excellent or good for 20 (83.3%) procedures and fair (Fair intraoperative blood loss was more than expected for the type of procedure performed) for 2 (8.3%) procedures; the rating was unknown for 1 procedure and not done for 1 procedure. Both procedures requiring surgical drains with fair ratings were major orthopedic surgeries.

Routine Prophylaxis Study

In a multicenter, open-label, prospective, randomized, controlled postmarketing clinical trial of ADVATE use in two prophylactic treatment regimens compared to that of on-demand treatment, 53 PTPs with severe to moderately severe hemophilia A (FVIII level ≤2 IU/dL) were analyzed in the per-protocol group. Subjects were initially treated for 6 months of on-demand therapy and then randomized to 12 months of either a standard prophylaxis regimen (20 to 40 IU/kg every 48 hours) or PK-driven prophylaxis regimen (20 to 80 IU/kg every 72 hours). All subjects had a history of at least 8 joint bleeding episodes per year upon entering the trial. Each subject in the per-protocol group was adherent to >90% of the prescribed number of prophylactic infusions; no subject in the trial surpassed the upper boundary of 110% of the prescribed number of prophylactic infusions.

The equation used to determine the weight-adjusted dose of the product used in the PK-driven prophylaxis arm, as calculated from the individual subject's incremental recovery and half-life values to achieve a trough level of ≥1 IU/dL at the inter-dosing interval of 72 hours is defined as follows:

Di = (2)72/ti / ri (i is the subject)
D = target FVIII dose (IU/kg) that ensures that a trough level of ≥1 IU/dL is achieved after 72 hours
  r = FVIII incremental recovery (IU/dL / IU/kg) as determined by the subject's PK analysis
  t = FVIII half-life (hrs) as determined by the subject's PK analysis

The median annual bleed rate during the on-demand therapy period was 44 bleeds per subject per year compared to 1 bleed per subject per year while on either prophylaxis regimen, which was a statistically significant difference (p<0.0001). Twenty-two of 53 (42%) subjects experienced no bleeding episodes while on prophylaxis for one year. While there was no statistically significant difference in bleeding frequency observed between the two prophylaxis regimens studied, the trial was not powered to demonstrate equivalence in bleeding rate between the two prophylaxis arms.

Table 9: Annual Bleed Rate of Prophylaxis Compared to On-Demand Treatment
Clinical Parameters | On-Demand (n=53) | Standard Prophylaxis (n=30) | PK-Driven Prophylaxis (n=23) | Either Standard or PK-Driven Prophylaxis (n=53)
Median (IQR) [Inter-quartile-range (IQR) is defined as the difference between the 75th percentile (3rd quartile) and the 25th percentile (first quartile).] Annual Bleed Rate(ABR) | 44.0 (20.8) | 1.0 (2.1) | 1.0 (4.1) | 1.0 (4.1)
Median (IQR) Joint ABR | 38.7 (24.8) | 0.5 (2.0) | 1.0 (4.1) | 1.0 (2.1)
Median (IQR) Non-Joint ABR^1 | 4.0 (11.9) | 0.0 (0.0) | 0.0 (0.0) | 0.0 (0.0)
Median (IQR) Spontaneous ABR | 32.0 (26.8) | 0.0 (1.9) | 0.0 (2.0) | 0.0 (1.9)
Median (IQR) Traumatic ABR | 11.5 (17.2) | 0.0 (1.0) | 1.0 (1.0) | 0.0 (1.0)

The annualized bleed rates by age category during on-demand and either standard or PK-driven prophylaxis regimens are shown in Table 10.

Table 10: Annualized Bleed Rate by Age Category and Any Prophylaxis vs On-Demand (Per Protocol)
 |  | Any Prophylaxis |  | On-Demand
Age Category | Number of Subjects | Median | Percentage of Subjects with Zero Bleeds | Median | Percentage of Subjects with Zero Bleeds
Children (≥7 to <12 years old) | 3 | 5.2 | 33% | 44.0 | All subjects bleed during On-Demand
Adolescents (≥12 to <16 years old) | 4 | 5.0 | 25% | 58.0 | All subjects bleed during On-Demand
Adults (≥16 years old and older) | 46 | 1.0 | 43% | 44.7 | All subjects bleed during On-Demand
All Subjects | 53 | 1.0 | 42% | 44.0 | All subjects bleed during On-Demand

As a secondary endpoint, the trial assessed all Short Form Health Survey (SF-36v1) domains. The SF-36v1 is a valid and reliable measure of health-related quality of life that is comprised of 8 domains categorized into 2 summary scores (Table 11).

Table 11: Mean Change in SF-36v1 Health Domain Scores Between End of On-Demand and End of Prophylaxis Treatment Regimens [Positive change values are in the favorable direction.]
SF-36v1 Health Domain | Mean Change | 95% Confidence Interval
Physical Functioning (PF) | 0.89 | (-1.02, 2.81)
Role Physical (RP) | 3.56 | (0.32, 6.79)
Bodily Pain (BP) | 4.13 | (1.63, 6.62)
General Health (GH) | 1.36 | (-0.72, 3.45)
Physical Component Score | 3.56 | (1.56, 5.56)
Vitality (VT) | 0.21 | (-2.22, 2.63)
Social Functioning (SF) | 1.72 | (-0.57, 4.00)
Role Emotional (RE) | -1.29 | (-3.78, 1.19)
Mental Health (MH) | -0.20 | (-2.89, 2.49)
Mental Component Score | -1.22 | (-3.66, 1.23)

Human Factors Usability Study

A human factors study was performed with 44 participants to evaluate the usability of the ADVATE in the BAXJECT III reconstitution system. Participants in the study included 15 patients, 16 caregivers, and 13 healthcare providers.

During the study, participants viewed an instructional video then performed the reconstitution steps utilizing the Instructions For Use (IFU). Objective performance data were collected and evaluated. Participants' comments from a postevaluation interview were reviewed for their appropriateness and applicability. As a result, the content of the package insert was revised to clarify the instructions for use.

15 REFERENCES

1. Fischer K, Collins P, Björkman S, Blanchette V, Oh M, Fritsch S, Schroth P, Spotts G, Ewenstein B. Trends in bleeding patterns during prophylaxis for severe haemophilia: observations from a series of prospective clinical trials. Haemophilia 2011 17(3):433-8.
2. Collins PW, Blanchette VS, Fischer K, Björkman S, Oh M, Fritsch S, Schroth P, Astermark J, Spotts G, Ewenstein B, The rAHF-PFM Study Group. Break-through bleeding in relation to predicted factor VIII levels in patients receiving prophylactic treatment for severe haemophilia A. J Thromb Haemost 2009 7(3):413-20.
3. Tarantino MD, Collins PW, Hay PW et al. Clinical evaluation of an advanced category antihaemophilic factor prepared using a plasma/albumin-free method: pharmacokinetics, efficacy, and safety in previously treated patients with haemophilia A. Haemophilia 2004 10:428-437.
4. Björkman S, Blanchette VS, Fischer K, Oh M, Spotts G, Schroth P, Fritsch S, Patrone L, Ewenstein BM, Collins PW, ADVATE Clinical Program Group. Comparative pharmacokinetics of plasma- and albumin-free recombinant factor VIII in children and adults: the influence of blood sampling schedule on observed age-related differences and implications for dose tailoring. J Thromb Haemost 2010 8(4):730-6.
5. Negrier C, Shapiro A, Berntorp E et al. Surgical evaluation of a recombinant factor VIII prepared using a plasma/albumin-free method: efficacy and safety of ADVATE in previously treated patients. Thromb.Haemost 2008 100:217-223.

16 HOW SUPPLIED/STORAGE AND HANDLING

How Supplied

ADVATE in a BAXJECT III system is packaged with 2 mL or 5 mL of Sterile Water for Injection, one Terumo Microbore Infusion set (2 mL only), one full prescribing physician insert, and one patient insert.

ADVATE is available in single-dose vials that contain the following nominal product strengths:

Nominal Strength | Factor VIII Potency Range | Potency Color Code | Carton NDC (Includes 2 mL sWFI Diluent) | Carton NDC (Includes 5 mL sWFI Diluent)
250 IU | 200 to 400 IU per vial | Light blue | 0944-3051-02
500 IU | 401 to 800 IU per vial | Pink | 0944-3052-02
1000 IU | 801 to 1200 IU per vial | Green | 0944-3053-02
1500 IU | 1201 to 1800 IU per vial | Purple | 0944-3054-02
2000 IU | 1801 to 2400 IU per vial | Orange |  | 0944-3045-10
3000 IU | 2401 to 3600 IU per vial | Silver |  | 0944-3046-10
4000 IU | 3601 to 4800 IU per vial | Dark Green |  | 0944-3047-10

Actual factor VIII activity in International Units is stated on the label of each ADVATE housing or carton.

Not made with natural rubber latex.

Storage and Handling

- Refrigerate ADVATE in powder form at 2° - 8°C (36° - 46°F).
- Store at room temperature up to 30°C (86°F) for a period of up to 6 months not to exceed the expiration date.
- Record on the carton the date ADVATE is removed from refrigeration. The product must not be returned to refrigerated temperature.
- Do not use beyond the expiration date printed on the ADVATE label or carton.
- Do not freeze.

17 PATIENT COUNSELING INFORMATION

- Advise the patient to read the FDA-approved patient labeling (Patient Information and Instructions for Use).
- Advise patients to report any adverse reactions or problems following ADVATE administration to their physician or healthcare provider.
- Allergic-type hypersensitivity reactions have been reported with ADVATE. Warn patients of the early signs of hypersensitivity reactions, including hives, pruritus, generalized urticaria, angioedema, hypotension, shock, anaphylaxis and acute respiratory distress. Advise patients to discontinue use of the product if these symptoms occur and seek immediate emergency treatment.
- Inhibitor formation may occur with the treatment of a patient with hemophilia A. Advise patients to contact their physician or treatment center if they experience a lack of clinical response to factor VIII replacement therapy, as this may be a manifestation of an inhibitor.
- Advise patients to consult with their physicians or healthcare provider prior to travel. While traveling, advise patients to bring an adequate supply of ADVATE based on their current regimen of treatment.

To enroll in the confidential, industry-wide Patient Notification System, call 1-888-873-2838.

Takeda Pharmaceuticals U.S.A., Inc.
Cambridge, MA 02142
U.S. License No. 1898

ADVATE, BAXJECT and RECOMBINATE are registered trademarks of Baxalta Incorporated.

Takeda and are registered trademarks of Takeda Pharmaceutical Company Limited.

©2025 Takeda Pharmaceutical Company Limited. All rights reserved.

Patented: see www.takeda.com/en-us/patents

ADV372

Patient Information

ADVATE® (ad-vate)
[Antihemophilic Factor (Recombinant)]

This leaflet summarizes important information about ADVATE. Please read it carefully before using this medicine. This information does not take the place of talking with your healthcare provider, and it does not include all of the important information about ADVATE. If you have any questions after reading this, ask your healthcare provider.

What is the most important information I need to know about ADVATE?

Do not attempt to do an infusion to yourself unless you have been taught how by your healthcare provider or hemophilia center.

You must carefully follow your healthcare provider's instructions regarding the dose and schedule for infusing ADVATE so that your treatment will work best for you.

What is ADVATE?

ADVATE is a medicine used to replace clotting factor (factor VIII or antihemophilic factor) that is missing in people with hemophilia A (also called "classic" hemophilia). The product does not contain plasma or albumin. Hemophilia A is an inherited bleeding disorder that prevents blood from clotting normally.

ADVATE is used to prevent and control bleeding in adults and children (0 to16 years) with hemophilia A.

Your healthcare provider may give you ADVATE when you have surgery.

ADVATE can reduce the number of bleeding episodes in adults and children (0 to 16 years) when used regularly (prophylaxis).

ADVATE is not used to treat von Willebrand disease.

Who should not use ADVATE?

You should not use ADVATE if you:

- Are allergic to mice or hamsters.
- Are allergic to any ingredients in ADVATE.

Tell your healthcare provider if you are pregnant or breastfeeding because ADVATE may not be right for you.

How should I use ADVATE?

ADVATE is given directly into the bloodstream.

You may infuse ADVATE at a hemophilia treatment center, at your healthcare provider's office or in your home. You should be trained on how to do infusions by your healthcare provider or hemophilia treatment center. Many people with hemophilia A learn to infuse their ADVATE by themselves or with the help of a family member.

Your healthcare provider will tell you how much ADVATE to use based on your weight, the severity of your hemophilia A, and where you are bleeding.

You may have to have blood tests done after getting ADVATE to be sure that your blood level of factor VIII is high enough to clot your blood.

Call your healthcare provider right away if your bleeding does not stop after taking ADVATE.

What should I tell my healthcare provider before I use ADVATE?

You should tell your healthcare provider if you:

- Have or have had any medical problems.
- Take any medicines, including prescription and non-prescription medicines, such as over-the-counter medicines, supplements or herbal remedies.
- Have any allergies, including allergies to mice or hamsters.
- Are breastfeeding. It is not known if ADVATE passes into your milk and if it can harm your baby.
- Are pregnant or planning to become pregnant. It is not known if ADVATE may harm your unborn baby.
- Have been told that you have inhibitors to factor VIII (because ADVATE may not work for you).

What are the possible side effects of ADVATE?

You can have an allergic reaction to ADVATE.

Your body may form inhibitors to factor VIII. An inhibitor is part of the body's normal defense system. If you form inhibitors, it may stop ADVATE from working properly. Consult with your healthcare provider to make sure you are carefully monitored with blood tests for the development of inhibitors to factor VIII.

Call your healthcare provider right away and stop treatment if you get a rash or hives, itching, tightness of the throat, chest pain or tightness, difficulty breathing, lightheadedness, dizziness, nausea or fainting.

Side effects that have been reported with ADVATE include:

cough
sore throat
unusual taste
abdominal pain
diarrhea
nausea/vomiting

headache
fever
dizziness
hot flashes
chills
sweating

joint swelling/aching
itching
hematoma
swelling of legs
runny nose/congestion
rash

Tell your healthcare provider about any side effects that bother you or do not go away.

These are not all the possible side effects with ADVATE. You can ask your healthcare provider for information that is written for healthcare professionals.

What are the ADVATE dosage strengths?

ADVATE with 2 mL or 5 mL Sterile Water for Injection in a BAXJECT® III system comes in six different dosage strengths: 250 International Units (IU), 500 IU, 1000 IU, 1500 IU, 2000 IU, 3000 IU, and 4000 IU. The actual strength will be imprinted on the label on the housing and on the box. The six different strengths are color coded, as follows:

Dosage strength of approximately 250 International Units (200 to 400 IU) (with 2 mL sWFI)

Dosage strength of approximately 500 International Units (401 to 800 IU) (with 2 mL sWFI)

Dosage strength of approximately 1000 International Units (801 to 1200 IU) (with 2 mL sWFI)

Dosage strength of approximately 1500 International Units (1201 to 1800 IU) (with 2 mL sWFI)

Dosage strength of approximately 2000 International Units (1801 to 2400 IU) (with 5 mL sWFI)

Dosage strength of approximately 3000 International Units (2401 to 3600 IU) (with 5 mL sWFI)

Dosage strength of approximately 4000 International Units (3601 to 4800 IU) (with 5 mL sWFI)

Always check the actual dosage strength printed on the label to make sure you are using the strength prescribed by your healthcare provider. Always check the expiration date printed on the box. Do not use the product after the expiration date printed on the box.

How do I store ADVATE?

Do not freeze ADVATE.

Store ADVATE in a refrigerator (2° to 8°C [36° to 46°F]) or at room temperature (up to 30°C [86°F]) for up to 6 months.

If you choose to store ADVATE at room temperature:

- Note the date that the product is removed from refrigeration on the box.
- Do not use after six months from this date or after the expiration date.
- Do not return the product back to the refrigerator.

Store ADVATE in the original box and protect from extreme exposure to light.

Reconstituted product (after mixing dry product with wet diluent) must be used within 3 hours and cannot be stored or refrigerated. Discard any unused ADVATE at the end of your infusion.

What else should I know about ADVATE and Hemophilia A?

Medicines are sometimes prescribed for purposes other than those listed here. Do not use ADVATE for a condition for which it is not prescribed. Do not share ADVATE with other people, even if they have the same symptoms that you have.

Resources at Takeda available to the patients:

For more product information on ADVATE, please visit www.ADVATE.com or call 1-877-TAKEDA-7 (1-877-825-3327).

Takeda Pharmaceuticals U.S.A., Inc.
Cambridge, MA 02142
U.S. License No. 1898

ADVATE and BAXJECT are registered trademarks of Baxalta Incorporated.

Takeda and are registered trademarks of Takeda Pharmaceutical Company Limited.

©2025 Takeda Pharmaceutical Company Limited. All rights reserved.

Patented: see www.takeda.com/en-us/patents

Revised: 3/2025
ADV372

Instructions For Use

ADVATE®
[Antihemophilic Factor (Recombinant)]
(For intravenous use only)

Do not attempt to do an infusion to yourself unless you have been taught how by your healthcare provider or hemophilia center.

See below for step-by-step instructions for reconstituting ADVATE in a BAXJECT® III system.

- Always follow the specific instructions given by your healthcare provider. The steps listed below are general guidelines for using ADVATE. If you are unsure of the procedures, please call your healthcare provider before using.
- Call your healthcare provider right away if bleeding is not controlled after using ADVATE.
- Your healthcare provider will prescribe the dose that you should take.
- Your healthcare provider may need to take blood tests from time to time.
- Talk to your healthcare provider before traveling. Plan to bring enough ADVATE for your treatment during this time.
- Dispose of all materials, including any leftover reconstituted ADVATE product, in an appropriate container.

1. Prepare a clean flat surface and gather all the materials you will need for the infusion. Check the expiration date, and let the ADVATE warm up to room temperature. Wash your hands and put on clean exam gloves. If infusing yourself at home, the use of gloves is optional.
2. Open the ADVATE package by peeling away the lid. Remove the ADVATE from the package and visually inspect the contents of the product and diluent vial. The ADVATE powder should be white to off-white in color and the diluent should not contain particles. Do not use if discoloration or particles are seen.
3. Place on a flat surface with the diluent vial on top. The diluent vial has a blue stripe.
4. With one hand holding the ADVATE housing, press down firmly on the diluent vial with the other hand until the system is fully collapsed and the diluent flows down into the ADVATE vial. Both vials will move into the housing when pressed. If you don't see the diluent transfer to the product vial, press the vials again to assure they are completely inserted. Do not remove the blue cap until instructed in a later step.
5. Swirl the ADVATE gently and continuously until the ADVATE is completely dissolved. Do not shake. Do not refrigerate after reconstitution. Inspect the ADVATE solution for particulate matter and discoloration prior to administration. The solution should be clear and colorless in appearance. If not, do not use the solution and notify your healthcare provider immediately.
6. Take off the blue cap from the housing and connect the syringe. Be careful to not inject air into the ADVATE.
7. Turn over the ADVATE so that the vial containing the ADVATE solution is on top. Draw the ADVATE solution into the syringe by pulling back the plunger slowly. If the solution does not draw into the syringe, be sure that both vials are pressed firmly together. The contents of more than one vial may be drawn into a single, appropriately sized syringe if you are using more than one vial of ADVATE.
8. Disconnect the syringe from the system. Attach the infusion needle to the syringe using a winged (butterfly) infusion set, if available. Point the needle up and remove any air bubbles by gently tapping the syringe with your finger and slowly and carefully pushing air out of the syringe and needle.
9. Apply a tourniquet and get the injection site ready by wiping the skin well with an alcohol swab (or other suitable solution suggested by your healthcare provider or hemophilia center).
10. Insert the needle into the vein and remove the tourniquet. Slowly infuse the ADVATE. Do not infuse any faster than 10 mL per minute.
11. Take the needle out of the vein and use sterile gauze to put pressure on the infusion site for several minutes.
12. Do not recap the needle. Place the needle, syringe, and ADVATE in a hard-walled sharps container for proper disposal. Do not dispose of these supplies in ordinary household trash.
13. Remove the peel-off label from the housing and place it in your logbook. Clean any spilled blood with a freshly prepared mixture of 1 part bleach and 9 parts water, soap and water, or any household disinfecting solution.

Important: Contact your healthcare provider or local hemophilia treatment center if you experience any problems.

Takeda Pharmaceuticals U.S.A., Inc.
Cambridge, MA 02142
U.S. License No. 1898

ADVATE and BAXJECT are registered trademarks of Baxalta Incorporated.

Takeda and are registered trademarks of Takeda Pharmaceutical Company Limited.

©2025 Takeda Pharmaceutical Company Limited. All rights reserved.

Patented: see www.takeda.com/en-us/patents

Revised: 3/2025
ADV372

PRINCIPAL DISPLAY PANEL - 250 IU 2 mL Kit Carton

ADVATE®
[Antihemophilic Factor (Recombinant)]

NDC 0944-3051-02

Single-dose only

For Intravenous Administration Only
Rx Only

Lyophilized powder for reconstitution

ADVATE and diluent preassembled in BAXJECT III system

Product does not contain plasma/albumin

ACTUAL POTENCY

2
mL

Takeda

PRINCIPAL DISPLAY PANEL - 250 IU 2 mL Blister Pack Label

ADVATE®
[Antihemophilic Factor (Recombinant)]

NDC 0944-3051-03

For Intravenous Administration Only

ADVATE and diluent preassembled in
BAXJECT® III system

Do not open until time of use

Do not use if packaging is opened or damaged

Discard unused portion.

Rx Only

2
mL

Product does not contain plasma/albumin

Single-dose only

Takeda

6521200

IU:

LOT:

EXP:

PRINCIPAL DISPLAY PANEL - 250 IU 2 mL Container Label

ADVATE®
[Antihemophilic Factor (Recombinant)]

For Intravenous Administration Only
Rx Only

ADVATE and diluent preassembled in BAXJECT® III system

Directions for use: see package insert

Product does not contain
plasma/albumin

6521198

Takeda

IU:

LOT:

EXP:

PRINCIPAL DISPLAY PANEL - 500 IU 2 mL Kit Carton

ADVATE®
[Antihemophilic Factor (Recombinant)]

NDC 0944-3052-02

Single-dose only

For Intravenous Administration Only
Rx Only

Lyophilized powder for reconstitution

ADVATE and diluent preassembled in BAXJECT III system

Product does not contain plasma/albumin

ACTUAL POTENCY

2
mL

Takeda

PRINCIPAL DISPLAY PANEL - 500 IU 2 mL Blister Pack Label

ADVATE®
[Antihemophilic Factor (Recombinant)]

NDC 0944-3052-03

For Intravenous Administration Only

ADVATE and diluent preassembled in
BAXJECT® III system

Do not open until time of use

Do not use if packaging is opened or damaged

Discard unused portion.

Rx Only

2
mL

Product does not contain plasma/albumin

Single-dose only

Takeda

6521235

IU:

LOT:

EXP:

PRINCIPAL DISPLAY PANEL - 500 IU 2 mL Container Label

ADVATE®
[Antihemophilic Factor (Recombinant)]

For Intravenous Administration Only
Rx Only

ADVATE and diluent preassembled in BAXJECT® III system

Directions for use: see package insert

Product does not contain
plasma/albumin

6521234

Takeda

IU:

LOT:

EXP:

PRINCIPAL DISPLAY PANEL - 1000 IU 2 mL Kit Carton

ADVATE®
[Antihemophilic Factor (Recombinant)]

NDC 0944-3053-02

Single-dose only

For Intravenous Administration Only
Rx Only

Lyophilized powder for reconstitution

ADVATE and diluent preassembled in BAXJECT III system

Product does not contain plasma/albumin

ACTUAL POTENCY

2
mL

Takeda

PRINCIPAL DISPLAY PANEL - 1000 IU 2 mL Blister Pack Label

ADVATE®
[Antihemophilic Factor (Recombinant)]

NDC 0944-3053-03

For Intravenous Administration Only

ADVATE and diluent preassembled in
BAXJECT® III system

Do not open until time of use

Do not use if packaging is opened or damaged

Discard unused portion.

Rx Only

2
mL

Product does not contain plasma/albumin

Single-dose only

Takeda

6521242

IU:

LOT:

EXP:

PRINCIPAL DISPLAY PANEL - 1000 IU 2 mL Container Label

ADVATE®
[Antihemophilic Factor (Recombinant)]

For Intravenous Administration Only
Rx Only

ADVATE and diluent preassembled in BAXJECT® III system

Directions for use: see package insert

Product does not contain
plasma/albumin

6521239

Takeda

IU:

LOT:

EXP:

PRINCIPAL DISPLAY PANEL - 1500 IU 2 mL Kit Carton

ADVATE®
[Antihemophilic Factor (Recombinant)]

NDC 0944-3054-02

Single-dose only

For Intravenous Administration Only
Rx Only

Lyophilized powder for reconstitution

ADVATE and diluent preassembled in BAXJECT III system

Product does not contain plasma/albumin

ACTUAL POTENCY

2
mL

Takeda

PRINCIPAL DISPLAY PANEL - 1500 IU 2 mL Blister Pack Label

ADVATE®
[Antihemophilic Factor (Recombinant)]

NDC 0944-3054-03

For Intravenous Administration Only

ADVATE and diluent preassembled in
BAXJECT® III system

Do not open until time of use

Do not use if packaging is opened or damaged

Discard unused portion.

Rx Only

2
mL

Product does not contain plasma/albumin

Single-dose only

Takeda

6521276

IU:

LOT:

EXP:

PRINCIPAL DISPLAY PANEL - 1500 IU 2 mL Container Label

ADVATE®
[Antihemophilic Factor (Recombinant)]

For Intravenous Administration Only
Rx Only

ADVATE and diluent preassembled in BAXJECT® III system

Directions for use: see package insert

Product does not contain
plasma/albumin

6521260

Takeda

IU:

LOT:

EXP:

PRINCIPAL DISPLAY PANEL - 2000 IU 5 mL Kit Carton

ADVATE®
[Antihemophilic Factor (Recombinant)]

NDC 0944-3045-10

Single-dose only

For Intravenous Administration Only
Rx Only

Lyophilized powder for reconstitution

ADVATE and diluent preassembled in BAXJECT III system

Product does not contain plasma/albumin

ACTUAL POTENCY

5
mL

Takeda

PRINCIPAL DISPLAY PANEL - 2000 IU 5 mL Blister Pack Label

ADVATE®
[Antihemophilic Factor (Recombinant)]

NDC 0944-3045-11

For Intravenous Administration Only

ADVATE and diluent preassembled in
BAXJECT® III system

Do not open until time of use

Do not use if packaging is opened or damaged

Discard unused portion.

Rx Only

5
mL

Product does not contain plasma/albumin

Single-dose only

Takeda

6521302

IU:

LOT:

EXP:

PRINCIPAL DISPLAY PANEL - 2000 IU 5 mL Container Label

ADVATE®
[Antihemophilic Factor (Recombinant)]

For Intravenous Administration Only
Rx Only

ADVATE and diluent preassembled in BAXJECT® III system

Directions for use: see package insert

Product does not contain
plasma/albumin

6521293

Takeda

IU:

LOT:

EXP:

PRINCIPAL DISPLAY PANEL - 3000 IU 5 mL Kit Carton

ADVATE®
[Antihemophilic Factor (Recombinant)]

NDC 0944-3046-10

Single-dose only

For Intravenous Administration Only
Rx Only

Lyophilized powder for reconstitution

ADVATE and diluent preassembled in BAXJECT III system

Product does not contain plasma/albumin

ACTUAL POTENCY

5
mL

Takeda

PRINCIPAL DISPLAY PANEL - 3000 IU 5 mL Blister Pack Label

ADVATE®
[Antihemophilic Factor (Recombinant)]

NDC 0944-3046-11

For Intravenous Administration Only

ADVATE and diluent preassembled in
BAXJECT® III system

Do not open until time of use

Do not use if packaging is opened or damaged

Discard unused portion.

Rx Only

5
mL

Product does not contain plasma/albumin

Single-dose only

Takeda

6521323

IU:

LOT:

EXP:

PRINCIPAL DISPLAY PANEL - 3000 IU 5 mL Container Label

ADVATE®
[Antihemophilic Factor (Recombinant)]

For Intravenous Administration Only
Rx Only

ADVATE and diluent preassembled in BAXJECT® III system

Directions for use: see package insert

Product does not contain
plasma/albumin

6521316

Takeda

IU:

LOT:

EXP:

PRINCIPAL DISPLAY PANEL - 4000 IU 5 mL Kit Carton

ADVATE®
[Antihemophilic Factor (Recombinant)]

NDC 0944-3047-10

Single-dose only

For Intravenous Administration Only
Rx Only

Lyophilized powder for reconstitution

ADVATE and diluent preassembled in BAXJECT III system

Product does not contain plasma/albumin

ACTUAL POTENCY

5
mL

Takeda

PRINCIPAL DISPLAY PANEL - 4000 IU 5 mL Blister Pack Label

ADVATE®
[Antihemophilic Factor (Recombinant)]

NDC 0944-3047-11

For Intravenous Administration Only

ADVATE and diluent preassembled in
BAXJECT® III system

Do not open until time of use

Do not use if packaging is opened or damaged

Discard unused portion.

Rx Only

5
mL

Product does not contain plasma/albumin

Single-dose only

Takeda

6521345

IU:

LOT:

EXP:

PRINCIPAL DISPLAY PANEL - 4000 IU 5 mL Container Label

ADVATE®
[Antihemophilic Factor (Recombinant)]

For Intravenous Administration Only
Rx Only

ADVATE and diluent preassembled in BAXJECT® III system

Directions for use: see package insert

Product does not contain
plasma/albumin

6521338

Takeda

IU:

LOT:

EXP:

PRINCIPAL DISPLAY PANEL - Advate Vial Label

Antihemophilic Factor (Recombinant)

Takeda

0754067

Lot No.:

PRINCIPAL DISPLAY PANEL - Sterile Water for Injection Vial Label

Sterile Water for Injection

Lot No.:

Siegfried Hameln GmbH

0742211